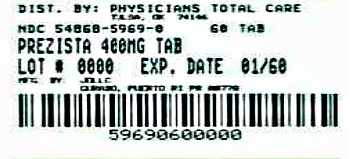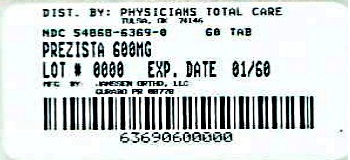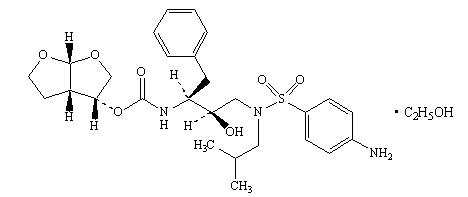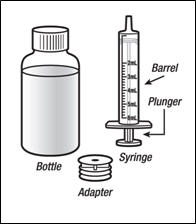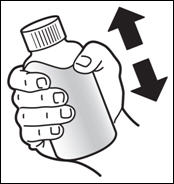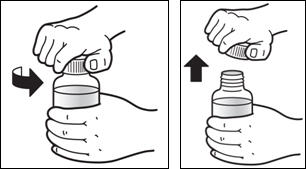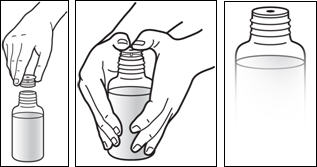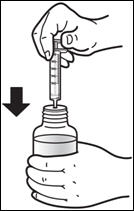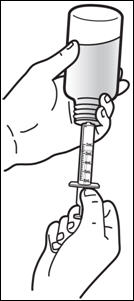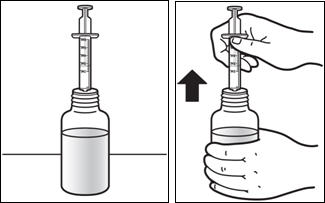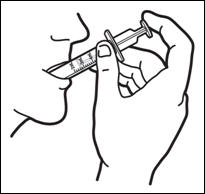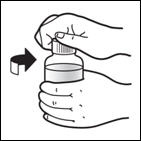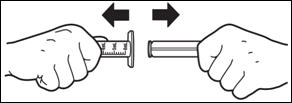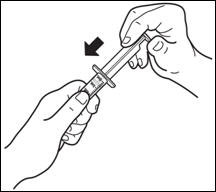 DRUG LABEL: PREZISTA
NDC: 54868-5969 | Form: TABLET, FILM COATED
Manufacturer: Physicians Total Care, Inc.
Category: prescription | Type: HUMAN PRESCRIPTION DRUG LABEL
Date: 20121022

ACTIVE INGREDIENTS: darunavir ethanolate 400 mg/1 1
INACTIVE INGREDIENTS: silicon dioxide; crospovidone; magnesium stearate; cellulose, microcrystalline; FD&C Yellow No. 6; polyethylene glycol 3350; polyvinyl alcohol; talc; titanium dioxide

HIGHLIGHTS OF PRESCRIBING INFORMATION

These highlights do not include all the information needed to use PREZISTA safely and effectively. See Full Prescribing Information for PREZISTA.
PREZISTA (darunavir) Oral Suspension, for Oral use
PREZISTA (darunavir) Tablet, Film Coated for Oral use
Initial U.S. Approval – 2006

RECENT MAJOR CHANGES

• Indications and Usage • Pediatric Patients (1.2) | 12/2011
• Dosage and Administration • Adult Patients (2.1) | 12/2011
• Pediatric Patients (2.2) | 12/2011
• Warnings and Precautions • Severe Skin Reactions (5.3) | 06/2012
• Immune Reconstitution Syndrome (5.8) | 02/2012
• Pediatric Patients (5.11) | 12/2011

1 INDICATIONS AND USAGE

PREZISTA is a human immunodeficiency virus (HIV-1) protease inhibitor indicated for the treatment of HIV-1 infection in adult patients. PREZISTA is also indicated for the treatment of HIV-1 infection in pediatric patients 3 years of age and older. PREZISTA must be co-administered with ritonavir (PREZISTA/ritonavir) and with other antiretroviral agents. (1)

2 DOSAGE AND ADMINISTRATION

- Treatment-naïve adult patients and treatment-experienced adult patients with no darunavir resistance associated substitutions: 800 mg (two 400 mg tablets) taken with ritonavir 100 mg once daily and with food. (2.1)
- Treatment-experienced adult patients with at least one darunavir resistance associated substitution: 600 mg (one 600 mg tablet) taken with ritonavir 100 mg twice daily and with food. (2.1)
- Pediatric patients (3 to less than 18 years of age and weighing at least 10 kg): dosage of PREZISTA and ritonavir is based on body weight and should not exceed the treatment-experienced adult dose. Do not use once daily dosing in pediatric patients. PREZISTA should be taken with ritonavir twice daily and with food. (2.2)
- PREZISTA/ritonavir is not recommended for use in patients with severe hepatic impairment. (2.3)

3 DOSAGE FORMS AND STRENGTHS

- 100 mg/mL oral suspension (3)
- 75 mg tablets, 150 mg tablets, 400 mg tablets, and 600 mg tablets (3)

4 CONTRAINDICATIONS

Co-administration with alfuzosin, dihydroergotamine, ergonovine, ergotamine, methylergonovine, cisapride, pimozide, oral midazolam, triazolam, St. John's Wort, lovastatin, simvastatin, rifampin and sildenafil (for treatment of pulmonary arterial hypertension). (4)

- Due to the need for co-administration of PREZISTA with ritonavir, please refer to ritonavir prescribing information for a description of ritonavir contraindications. (4)

5 WARNINGS AND PRECAUTIONS

- Drug-induced hepatitis (e.g., acute hepatitis, cytolytic hepatitis) has been reported with PREZISTA/ritonavir. Monitor liver function before and during therapy, especially in patients with underlying chronic hepatitis, cirrhosis, or in patients who have pre-treatment elevations of transaminases. Post-marketing cases of liver injury, including some fatalities, have been reported. (5.2, 6)
- Skin reactions ranging from mild to severe, including Stevens-Johnson Syndrome, toxic epidermal necrolysis and acute generalized exanthematous pustulosis, have been reported. Discontinue treatment if severe reaction develops. (5.3, 6)
- Use with caution in patients with a known sulfonamide allergy. (5.4)
- Patients may develop new onset diabetes mellitus or hyperglycemia. Initiation or dose adjustments of insulin or oral hypoglycemic agents may be required. (5.6)
- Patients may develop redistribution/accumulation of body fat (5.7) or immune reconstitution syndrome. (5.8)
- Patients with hemophilia may develop increased bleeding events. (5.9)
- PREZISTA/ritonavir should not be used in pediatric patients below 3 years of age in view of toxicity and mortality observed in juvenile rats dosed with darunavir up to days 23 to 26 of age. (5.11)

6 ADVERSE REACTIONS

- The most common clinical adverse drug reactions to PREZISTA/ritonavir (incidence greater than or equal to 5%) of at least moderate intensity (greater than or equal to Grade 2) were diarrhea, nausea, rash, headache, abdominal pain and vomiting. (6)

To report SUSPECTED ADVERSE REACTIONS, contact Janssen Products, LP at 1-800-JANSSEN (1-800-526-7736) or FDA at 1-800-FDA-1088 or www.fda.gov/medwatch.

7 DRUG INTERACTIONS

- Co-administration of PREZISTA/ritonavir with other drugs can alter the concentration of other drugs and other drugs may alter the concentrations of darunavir. The potential drug-drug concentrations must be considered prior to and during therapy. (4, 5.5, 7, 12.3).

8 USE IN SPECIFIC POPULATIONS

- Use during pregnancy only if the potential benefit justifies the potential risk. (8.1)
  - Pregnancy Registry available. (8.1)
- Mothers should be instructed not to breastfeed due to the potential for HIV transmission and the potential for serious adverse reactions in nursing infants. (8.3)

FULL PRESCRIBING INFORMATION

1 INDICATIONS AND USAGE

1.1 Adult Patients

PREZISTA®, co-administered with ritonavir (PREZISTA/ritonavir), and with other antiretroviral agents, is indicated for the treatment of human immunodeficiency virus (HIV-1) infection.

This indication is based on analyses of plasma HIV-1 RNA levels and CD4+ cell counts from 2 controlled Phase 3 trials of 48 weeks duration in antiretroviral treatment-naïve and treatment-experienced patients and 2 controlled Phase 2 trials of 96 weeks duration in clinically advanced, treatment-experienced adult patients.

1.2 Pediatric Patients

PREZISTA, co-administered with ritonavir (PREZISTA/ritonavir), and with other antiretroviral agents, is indicated for the treatment of HIV-1 infection in pediatric patients 3 years of age and older [see Use in Specific Populations (8.4)].

This indication is based on 24-week analyses of plasma HIV-1 RNA levels and CD4+ cell counts from 2 open-label Phase 2 trials in antiretroviral treatment-experienced pediatric patients (one trial in patients 6 to less than 18 years of age and one trial in patients 3 to less than 6 years of age).

In treatment-experienced adult and pediatric patients, the following points should be considered when initiating therapy with PREZISTA/ritonavir:

- Treatment history and, when available, genotypic or phenotypic testing should guide the use of PREZISTA/ritonavir [see Clinical Pharmacology (12.4)].
- The use of other active agents with PREZISTA/ritonavir is associated with a greater likelihood of treatment response [see Clinical Pharmacology (12.4) and Clinical Studies (14.3)].

2 DOSAGE AND ADMINISTRATION

2.1 Adult Patients

PREZISTA must be co-administered with ritonavir to exert its therapeutic effect. Failure to correctly co-administer PREZISTA with ritonavir will result in plasma levels of darunavir that will be insufficient to achieve the desired antiviral effect and will alter some drug interactions.

Patients who have difficulty swallowing PREZISTA tablets can use the 100 mg/mL PREZISTA oral suspension.

Treatment-Naïve Adult Patients

The recommended oral dose of PREZISTA is 800 mg (two 400 mg tablets or 8 mL of the oral suspension) taken with ritonavir 100 mg (one 100 mg tablet/capsule or 1.25 mL of a 80 mg/mL ritonavir oral solution) once daily and with food.

Treatment-Experienced Adult Patients

Treatment-Experienced Adult Patients
With no darunavir resistance associated substitutions [V11I, V32I, L33F, I47V, I50V, I54L, I54M, T74P, L76V, I84V and L89V] | With at least one darunavir resistance associated substitution
PREZISTA 800 mg (two 400 mg tablets or 8 mL) once daily with ritonavir 100 mg (one 100 mg tablet/capsule or 1.25 mL) once daily and with food | PREZISTA 600 mg (e.g. one 600 mg tablet or 6 mL) twice daily with ritonavir 100 mg (one 100 mg tablet/capsule or 1.25 mL) twice daily and with food

For antiretroviral treatment-experienced patients genotypic testing is recommended. However, when genotypic testing is not feasible, PREZISTA/ritonavir 600/100 mg twice daily dosing is recommended.

2.2 Pediatric Patients (age 3 to less than 18 years)

Do not use once daily dosing in pediatric patients.

Healthcare professionals should pay special attention to accurate dose selection of PREZISTA, transcription of the medication order, dispensing information and dosing instruction to minimize risk for medication errors, overdose, and underdose.

Prescribers should select the appropriate dose of PREZISTA/ritonavir for each individual child based on body weight (kg) and should not exceed the recommended dose for treatment-experienced adults.

Before prescribing PREZISTA, children weighing greater than or equal to 15 kg should be assessed for the ability to swallow tablets. If a child is unable to reliably swallow a tablet, the use of PREZISTA oral suspension should be considered.

The recommended dose of PREZISTA/ritonavir for pediatric patients (3 to less than 18 years of age and weighing at least 10 kg is based on body weight (see Tables 1, 2 and 3) and should not exceed the recommended treatment-experienced adult dose (PREZISTA/ritonavir 600/100 mg twice daily). PREZISTA should be taken with ritonavir twice daily and with food.

Dosing recommendations for pediatric patients weighing at least 10 kg but less than 15 kg

The weight-based dose in pediatric patients weighing less than 15 kg is PREZISTA 20 mg/kg with ritonavir 3 mg/kg which can be dosed using the following table:

Table 1: Recommended Dose for Pediatric Patients with PREZISTA Oral Suspension (100 mg/mL) and Ritonavir Oral Solution for Pediatric Patients Weighing 10 kg to Less Than 15 kg
Body weight (kg) | Dose (twice daily with food)
Greater than or equal to 10 kg to less than 11 kg | PREZISTA 200 mg (2 mL) with ritonavir 32 mg (0.4 mL)
Greater than or equal to 11 kg to less than 12 kg | PREZISTA 220 mg (2.2 mL) with ritonavir 32 mg (0.4 mL)
Greater than or equal to 12 kg to less than 13 kg | PREZISTA 240 mg (2.4 mL) with ritonavir 40 mg (0.5 mL)
Greater than or equal to 13 kg to less than 14 kg | PREZISTA 260 mg (2.6 mL) with ritonavir 40 mg (0.5 mL)
Greater than or equal to 14 kg to less than 15 kg | PREZISTA 280 mg (2.8 mL) with ritonavir 48 mg (0.6 mL)

Dosing recommendations for pediatric patients weighing at least 15 kg

Pediatric patients who weigh at least 15 kg and are able to swallow tablets can be dosed using the following table:

Table 2: Recommended Dose for Pediatric Patients with PREZISTA Tablets and Ritonavir Oral Solution or Tablets/Capsules for Pediatric Patients Weighing At Least 15 kg
Body Weight (kg) | Dose (twice daily with food)
Greater than or equal to 15 kg to less than 30 kg | PREZISTA 375 mg with ritonavir [with ritonavir oral solution: 80 mg/mL] 50 mg (0.6 mL)
Greater than or equal to 30 kg to less than 40 kg | PREZISTA 450 mg with ritonavir 60 mg (0.75 mL)
Greater than or equal to 40 kg | PREZISTA 600 mg with ritonavir100 mg

Pediatric patients who weigh at least 15 kg but are unable to swallow tablets can be dosed using the following table:

Table 3: Recommended Dose for Pediatric Patients with PREZISTA Oral Suspension (100 mg/mL) and Ritonavir Oral Solution for Pediatric Patients Weighing At Least 15 kg
Body Weight (kg) | Dose (twice daily with food)
Greater than or equal to 15 kg to less than 30 kg | PREZISTA 375 mg (3.8 mL) with ritonavir 50 mg (0.6 mL)
Greater than or equal to 30 kg to less than 40 kg | PREZISTA 450 mg (4.6 mL) with ritonavir 60 mg (0.75 mL)
Greater than or equal to 40 kg | PREZISTA 600 mg (6 mL) with ritonavir 100 mg (1.25 mL)

Do not use PREZISTA/ritonavir in pediatric patients below 3 years of age [see Warnings and Precautions (5.11) and Nonclinical Toxicology (13.2)].

2.3 Patients with Hepatic Impairment

No dose adjustment is required in patients with mild or moderate hepatic impairment. No data are available regarding the use of PREZISTA/ritonavir when co-administered to subjects with severe hepatic impairment; therefore, PREZISTA/ritonavir is not recommended for use in patients with severe hepatic impairment [see Use in Specific Populations (8.6) and Clinical Pharmacology (12.3)].

3 DOSAGE FORMS AND STRENGTHS

3.1 PREZISTA 100 mg/mL Oral Suspension

PREZISTA (darunavir) 100 mg/mL oral suspension is supplied as a white to off-white opaque suspension for oral use, containing darunavir ethanolate equivalent to 100 mg of darunavir per mL of suspension.

3.2 PREZISTA 75 mg Tablets

PREZISTA (darunavir) 75 mg tablets are supplied as white, caplet-shaped, film-coated tablets containing darunavir ethanolate equivalent to 75 mg of darunavir per tablet. Each tablet is debossed with "75" on one side and "TMC" on the other side.

3.3 PREZISTA 150 mg Tablets

PREZISTA (darunavir) 150 mg tablets are supplied as white, oval-shaped, film-coated tablets containing darunavir ethanolate equivalent to 150 mg of darunavir per tablet. Each tablet is debossed with "150" on one side and "TMC" on the other side.

3.4 PREZISTA 400 mg Tablets

PREZISTA (darunavir) 400 mg tablets are supplied as light orange, oval-shaped, film-coated tablets containing darunavir ethanolate equivalent to 400 mg of darunavir per tablet. Each tablet is debossed with "400MG" on one side and "TMC" on the other side.

3.5 PREZISTA 600 mg Tablets

PREZISTA (darunavir) 600 mg tablets are supplied as orange, oval-shaped, film-coated tablets containing darunavir ethanolate equivalent to 600 mg of darunavir per tablet. Each tablet is debossed with "600MG" on one side and "TMC" on the other side.

4 CONTRAINDICATIONS

Co-administration of PREZISTA/ritonavir is contraindicated with drugs that are highly dependent on CYP3A for clearance and for which elevated plasma concentrations are associated with serious and/or life-threatening events (narrow therapeutic index). These drugs and other contraindicated drugs (which may lead to reduced efficacy of darunavir) are listed in Table 4 [also see Drug Interactions (7.3), Table 9].

Table 4: Drugs That Are Contraindicated With PREZISTA/ritonavir
Drug Class | Drugs Within Class That Are Contraindicated With PREZISTA/ritonavir | Clinical Comment
Alpha 1-adrenoreceptor antagonist | Alfuzosin | Potential for serious and/or life-threatening reactions such as hypotension.
Ergot Derivatives | Dihydroergotamine, Ergonovine, Ergotamine, Methylergonovine | Potential for serious and/or life-threatening events such as acute ergot toxicity characterized by peripheral vasospasm and ischemia of the extremities and other tissues.
GI Motility Agent | Cisapride | Potential for serious and/or life-threatening reactions such as cardiac arrhythmias.
Neuroleptic | Pimozide | Potential for serious and/or life-threatening reactions such as cardiac arrhythmias.
Sedative/hypnotics | Orally administered Midazolam, Triazolam | Triazolam and orally administered midazolam are extensively metabolized by CYP3A. Co-administration of triazolam or orally administered midazolam with PREZISTA/ritonavir may cause large increases in the concentrations of these benzodiazepines. Potential for serious and/or life-threatening events such as prolonged or increased sedation or respiratory depression.
Herbal Products | St. John's Wort (Hypericum perforatum) | Patients taking PREZISTA/ritonavir should not use products containing St. John's wort because co-administration may result in reduced plasma concentrations of darunavir. This may result in loss of therapeutic effect and development of resistance.
HMG-CoA Reductase Inhibitors | Lovastatin, Simvastatin | Potential for serious reactions such as myopathy including rhabdomyolysis. For dosing recommendation regarding atorvastatin and pravastatin, see Table 9: Established and Other Potentially Significant Drug Interactions: Alterations in Dose or Regimen May Be Recommended Based on Drug Interaction Studies or Predicted Interaction.
Antimycobacterial | Rifampin | Rifampin is a potent inducer of CYP450 metabolism. PREZISTA/ritonavir should not be used in combination with rifampin, as this may cause significant decreases in darunavir plasma concentrations. This may result in loss of therapeutic effect to PREZISTA.
PDE-5 inhibitor | Sildenafil for treatment of pulmonary arterial hypertension | A safe and effective dose for the treatment of pulmonary arterial hypertension has not been established with PREZISTA/ritonavir. There is an increased potential for sildenafil-associated adverse events (which include visual disturbances, hypotension, prolonged erection, and syncope).

Due to the need for co-administration of PREZISTA with ritonavir, please refer to ritonavir prescribing information for a description of ritonavir contraindications.

5 WARNINGS AND PRECAUTIONS

5.1 General

PREZISTA must be co-administered with ritonavir and food to achieve the desired antiviral effect. Failure to administer PREZISTA with ritonavir and food may result in a loss of efficacy of darunavir.

Please refer to ritonavir prescribing information for additional information on precautionary measures.

5.2 Hepatotoxicity

Drug-induced hepatitis (e.g., acute hepatitis, cytolytic hepatitis) has been reported with PREZISTA/ritonavir. During the clinical development program (N=3063), hepatitis was reported in 0.5% of patients receiving combination therapy with PREZISTA/ritonavir. Patients with pre-existing liver dysfunction, including chronic active hepatitis B or C, have an increased risk for liver function abnormalities including severe hepatic adverse events.

Post-marketing cases of liver injury, including some fatalities, have been reported. These have generally occurred in patients with advanced HIV-1 disease taking multiple concomitant medications, having co-morbidities including hepatitis B or C co-infection, and/or developing immune reconstitution syndrome. A causal relationship with PREZISTA/ritonavir therapy has not been established.

Appropriate laboratory testing should be conducted prior to initiating therapy with PREZISTA/ritonavir and patients should be monitored during treatment. Increased AST/ALT monitoring should be considered in patients with underlying chronic hepatitis, cirrhosis, or in patients who have pre-treatment elevations of transaminases, especially during the first several months of PREZISTA/ritonavir treatment.

Evidence of new or worsening liver dysfunction (including clinically significant elevation of liver enzymes and/or symptoms such as fatigue, anorexia, nausea, jaundice, dark urine, liver tenderness, hepatomegaly) in patients on PREZISTA/ritonavir should prompt consideration of interruption or discontinuation of treatment.

5.3 Severe Skin Reactions

During the clinical development program (n=3063), severe skin reactions, accompanied by fever and/or elevations of transaminases in some cases, have been reported in 0.4% of subjects. Stevens-Johnson Syndrome was rarely (less than 0.1%) reported during the clinical development program. During post-marketing experience toxic epidermal necrolysis and acute generalized exanthematous pustulosis have been reported. Discontinue PREZISTA/ritonavir immediately if signs or symptoms of severe skin reactions develop. These can include but are not limited to severe rash or rash accompanied with fever, general malaise, fatigue, muscle or joint aches, blisters, oral lesions, conjunctivitis, hepatitis and/or eosinophilia.

Rash (all grades, regardless of causality) occurred in 10.3% of subjects treated with PREZISTA/ritonavir [also see Adverse Reactions (6)]. Rash was mostly mild-to-moderate, often occurring within the first four weeks of treatment and resolving with continued dosing. The discontinuation rate due to rash in subjects using PREZISTA/ritonavir was 0.5%.

Rash occurred more commonly in treatment-experienced subjects receiving regimens containing PREZISTA/ritonavir + raltegravir compared to subjects receiving PREZISTA/ritonavir without raltegravir or raltegravir without PREZISTA/ritonavir. However, rash that was considered drug related occurred at similar rates for all three groups. These rashes were mild to moderate in severity and did not limit therapy; there were no discontinuations due to rash.

5.4 Sulfa Allergy

Darunavir contains a sulfonamide moiety. PREZISTA should be used with caution in patients with a known sulfonamide allergy. In clinical studies with PREZISTA/ritonavir, the incidence and severity of rash were similar in subjects with or without a history of sulfonamide allergy.

5.5 Drug Interactions

See Table 4 for a listing of drugs that are contraindicated for use with PREZISTA/ritonavir due to potentially life-threatening adverse events, significant drug-drug interactions, or loss of therapeutic effect to PREZISTA [see Contraindications (4)]. Please refer to Table 9 for established and other potentially significant drug-drug interactions [see Drug Interactions (7.3)].

5.6 Diabetes Mellitus / Hyperglycemia

New onset diabetes mellitus, exacerbation of pre-existing diabetes mellitus, and hyperglycemia have been reported during postmarketing surveillance in HIV-infected patients receiving protease inhibitor (PI) therapy. Some patients required either initiation or dose adjustments of insulin or oral hypoglycemic agents for treatment of these events. In some cases, diabetic ketoacidosis has occurred. In those patients who discontinued PI therapy, hyperglycemia persisted in some cases. Because these events have been reported voluntarily during clinical practice, estimates of frequency cannot be made and causal relationships between PI therapy and these events have not been established.

5.7 Fat Redistribution

Redistribution/accumulation of body fat, including central obesity, dorsocervical fat enlargement (buffalo hump), peripheral wasting, facial wasting, breast enlargement, and "cushingoid appearance" have been observed in patients receiving antiretroviral therapy. The mechanism and long-term consequences of these events are currently unknown. A causal relationship has not been established.

5.8 Immune Reconstitution Syndrome

Immune reconstitution syndrome has been reported in patients treated with combination antiretroviral therapy, including PREZISTA. During the initial phase of combination antiretroviral treatment, patients whose immune systems respond may develop an inflammatory response to indolent or residual opportunistic infections (such as Mycobacterium avium infection, cytomegalovirus, Pneumocystis jirovecii pneumonia [PCP], or tuberculosis), which may necessitate further evaluation and treatment.

Autoimmune disorders (such as Graves' disease, polymyositis, and Guillain-Barré syndrome) have also been reported to occur in the setting of immune reconstitution; however, the time to onset is more variable, and can occur many months after initiation of antiretroviral treatment.

5.9 Hemophilia

There have been reports of increased bleeding, including spontaneous skin hematomas and hemarthrosis in patients with hemophilia type A and B treated with PIs. In some patients, additional factor VIII was given. In more than half of the reported cases, treatment with PIs was continued or reintroduced if treatment had been discontinued. A causal relationship between PI therapy and these episodes has not been established.

5.10 Resistance/Cross-Resistance

Because the potential for HIV cross-resistance among PIs has not been fully explored in PREZISTA/ritonavir treated patients, the effect therapy with PREZISTA will have on the activity of subsequently administered PIs is unknown [see Microbiology (12.4)].

5.11 Pediatric Patients

Do not administer PREZISTA/ritonavir in pediatric patients below 3 years of age in view of toxicity and mortality observed in juvenile rats dosed with darunavir (from 20 mg/kg to 1000 mg/kg) up to days 23 to 26 of age [see Use in Specific Populations (8.1 and 8.4), Clinical Pharmacology (12.3), and Nonclinical Toxicology (13.2)].

6 ADVERSE REACTIONS

The overall safety profile of PREZISTA/ritonavir 800/100 mg once daily and PREZISTA/ritonavir 600/100 mg twice daily is based on clinical trials and post-marketing data, and is consistent with the data presented below.

Because clinical trials are conducted under widely varying conditions, adverse reaction rates observed in the clinical trials of a drug cannot be directly compared to rates in the clinical trials of another drug and may not reflect the rates observed in practice.

Due to the need for co-administration of PREZISTA with ritonavir, please refer to ritonavir prescribing information for ritonavir-associated adverse reactions.

6.1 Clinical Trials Experience: Treatment-Naïve Adults

Study TMC114-C211

The safety assessment is based on all safety data from the Phase 3 trial TMC114-C211 comparing PREZISTA/ritonavir 800/100 mg once daily versus lopinavir/ritonavir 800/200 mg per day in 689 antiretroviral treatment-naïve HIV-1-infected adult subjects. The total mean exposure for subjects in the PREZISTA/ritonavir 800/100 mg once daily arm and in the lopinavir/ritonavir 800/200 mg per day arm was 162.5 and 153.5 weeks, respectively.

The majority of the adverse drug reactions (ADRs) reported during treatment with PREZISTA/ritonavir 800/100 mg once daily were mild in severity. The most common clinical ADRs to PREZISTA/ritonavir 800/100 mg once daily (greater than or equal to 5%) of at least moderate intensity (greater than or equal to Grade 2) were diarrhea, headache, abdominal pain and rash. 2.3% of subjects in the PREZISTA/ritonavir arm discontinued treatment due to ADRs.

ADRs to PREZISTA/ritonavir 800/100 mg once daily of at least moderate intensity (greater than or equal to Grade 2) in antiretroviral treatment-naïve HIV-1-infected adult subjects are presented in Table 5 and subsequent text below the table.

Table 5: Selected Clinical Adverse Drug Reactions to PREZISTA/ritonavir 800/100 mg Once Daily of at Least Moderate Intensity (≥ Grade 2) Occurring in ≥ 2% of Antiretroviral Treatment-Naïve HIV-1-Infected Adult Subjects
 | Randomized Study TMC114-C211
System Organ Class, Preferred Term, % | PREZISTA/ritonavir 800/100 mg once daily + TDF/FTC N = 343 | lopinavir/ritonavir 800/200 mg per day + TDF/FTC N = 346
Gastrointestinal Disorders
Abdominal pain | 6% | 6%
Diarrhea | 9% | 16%
Nausea | 4% | 4%
Vomiting | 2% | 4%
General Disorders and Administration Site Conditions
Fatigue | < 1% | 3%
Metabolism and Nutrition Disorders
Anorexia | 2% | < 1%
Nervous System Disorders
Headache | 7% | 6%
Skin and Subcutaneous Tissue Disorders
Rash | 6% | 7%
N=total number of subjects per treatment group
TDF = tenofovir disoproxil fumarate
FTC = emtricitabine

Less Common Adverse Reactions

Treatment-emergent ADRs of at least moderate intensity (greater than or equal to Grade 2) occurring in less than 2% of antiretroviral treatment-naïve subjects receiving PREZISTA/ritonavir 800/100 mg once daily are listed below by body system:

Gastrointestinal Disorders: acute pancreatitis, dyspepsia, flatulence

General Disorders and Administration Site Conditions: asthenia

Hepatobiliary Disorders: acute hepatitis (e.g., acute hepatitis, cytolytic hepatitis, hepatotoxicity)

Immune System Disorders: (drug) hypersensitivity, immune reconstitution syndrome

Metabolism and Nutrition Disorders: diabetes mellitus

Musculoskeletal and Connective Tissue Disorders: myalgia, osteonecrosis

Psychiatric Disorders: abnormal dreams

Skin and Subcutaneous Tissue Disorders: angioedema, pruritus, Stevens-Johnson Syndrome, urticaria

Laboratory abnormalities:

Selected Grade 2 to 4 laboratory abnormalities that represent a worsening from baseline observed in antiretroviral treatment-naïve adult subjects treated with PREZISTA/ritonavir 800/100 mg once daily are presented in Table 6.

Table 6: Grade 2 to 4 Laboratory Abnormalities Observed in Antiretroviral Treatment-Naïve HIV-1-Infected Adult Subjects
 |  | Randomized Study TMC114-C211
Laboratory Parameter Preferred Term, % | Limit | PREZISTA/ritonavir 800/100 mg once daily + TDF/FTC | lopinavir/ritonavir 800/200 mg per day + TDF/FTC
Biochemistry
Alanine Aminotransferase
Grade 2 | > 2.5 to ≤ 5.0 × ULN | 9% | 9%
Grade 3 | > 5.0 to ≤ 10.0 × ULN | 3% | 3%
Grade 4 | > 10.0 × ULN | < 1% | 3%
Aspartate Aminotransferase
Grade 2 | > 2.5 to ≤ 5.0 × ULN | 7% | 10%
Grade 3 | > 5.0 to ≤ 10.0 × ULN | 4% | 2%
Grade 4 | > 10.0 × ULN | 1% | 3%
Alkaline Phosphatase
Grade 2 | > 2.5 to ≤ 5.0 × ULN | 1% | 1%
Grade 3 | > 5.0 to ≤ 10.0 × ULN | 0% | < 1%
Grade 4 | > 10.0 × ULN | 0% | 0%
Hyperbilirubinemia
Grade 2 | > 1.5 to ≤ 2.5 × ULN | < 1% | 5%
Grade 3 | > 2.5 to ≤ 5.0 × ULN | < 1% | < 1%
Grade 4 | > 5.0 × ULN | 0% | 0%
Triglycerides
Grade 2 | 5.65–8.48 mmol/L 500–750 mg/dL | 3% | 10%
Grade 3 | 8.49–13.56 mmol/L 751–1200 mg/dL | 2% | 5%
Grade 4 | > 13.56 mmol/L > 1200 mg/dL | 1% | 1%
Total Cholesterol
Grade 2 | 6.20–7.77 mmol/L 240–300 mg/dL | 23% | 27%
Grade 3 | > 7.77 mmol/L > 300 mg/dL | 1% | 5%
Low-Density Lipoprotein Cholesterol
Grade 2 | 4.13–4.90 mmol/L 160–190 mg/dL | 14% | 12%
Grade 3 | ≥ 4.91 mmol/L ≥ 191 mg/dL | 9% | 6%
Elevated Glucose Levels
Grade 2 | 6.95–13.88 mmol/L 126–250 mg/dL | 11% | 10%
Grade 3 | 13.89–27.75 mmol/L 251–500 mg/dL | 1% | <1%
Grade 4 | > 27.75 mmol/L > 500 mg/dL | 0% | 0%
Pancreatic Lipase
Grade 2 | > 1.5 to ≤ 3.0 × ULN | 3% | 2%
Grade 3 | > 3.0 to ≤ 5.0 × ULN | < 1% | 1%
Grade 4 | > 5.0 × ULN | 0% | < 1%
Pancreatic Amylase
Grade 2 | > 1.5 to ≤ 2.0 × ULN | 5% | 2%
Grade 3 | > 2.0 to ≤ 5.0 × ULN | 5% | 4%
Grade 4 | > 5.0 × ULN | 0% | < 1%
N=total number of subjects per treatment group
TDF = tenofovir disoproxil fumarate
FTC = emtricitabine

6.2 Clinical Trials Experience: Treatment-Experienced Adults

Study TMC114-C214

The safety assessment is based on all safety data from the Phase 3 trial TMC114-C214 comparing PREZISTA/ritonavir 600/100 mg twice daily versus lopinavir/ritonavir 400/100 mg twice daily in 595 antiretroviral treatment-experienced HIV-1-infected adult subjects. The total mean exposure for subjects in the PREZISTA/ritonavir 600/100 mg twice daily arm and in the lopinavir/ritonavir 400/100 mg twice daily arm was 80.7 and 76.4 weeks, respectively.

The majority of the ADRs reported during treatment with PREZISTA/ritonavir 600/100 mg twice daily were mild in severity. The most common clinical ADRs to PREZISTA/ritonavir 600/100 mg twice daily (greater than or equal to 5%) of at least moderate intensity (greater than or equal to Grade 2) were diarrhea, nausea, rash, abdominal pain and vomiting. 4.7% of subjects in the PREZISTA/ritonavir arm discontinued treatment due to ADRs.

ADRs to PREZISTA/ritonavir 600/100 mg twice daily of at least moderate intensity (greater than or equal to Grade 2) in antiretroviral treatment-experienced HIV-1-infected adult subjects are presented in Table 7 and subsequent text below the table.

Table 7: Selected Clinical Adverse Drug Reactions to PREZISTA/ritonavir 600/100 mg Twice Daily of at Least Moderate Intensity (≥ Grade 2) Occurring in ≥ 2% of Antiretroviral Treatment-Experienced HIV-1-Infected Adult Subjects
 | Randomized Study TMC114-C214
System Organ Class, Preferred Term, % | PREZISTA/ritonavir 600/100 mg twice daily + OBR N = 298 | lopinavir/ritonavir 400/100 mg twice daily + OBR N = 297
Gastrointestinal Disorders
Abdominal distension | 2% | < 1%
Abdominal pain | 6% | 3%
Diarrhea | 14% | 20%
Dyspepsia | 2% | 1%
Nausea | 7% | 6%
Vomiting | 5% | 3%
General Disorders and Administration Site Conditions
Asthenia | 3% | 1%
Fatigue | 2% | 1%
Metabolism and Nutrition Disorders
Anorexia | 2% | 2%
Diabetes mellitus | 2% | < 1%
Nervous System Disorders
Headache | 3% | 3%
Skin and Subcutaneous Tissue Disorders
Rash | 7% | 3%
N=total number of subjects per treatment group
OBR = optimized background regimen

Less Common Adverse Reactions

Treatment-emergent ADRs of at least moderate intensity (greater than or equal to Grade 2) occurring in less than 2% of antiretroviral treatment-experienced subjects receiving PREZISTA/ritonavir 600/100 mg twice daily are listed below by body system:

Gastrointestinal Disorders: acute pancreatitis, flatulence

Musculoskeletal and Connective Tissue Disorders: myalgia

Psychiatric Disorders: abnormal dreams

Skin and Subcutaneous Tissue Disorders: pruritus, urticaria

Laboratory abnormalities:

Selected Grade 2 to 4 laboratory abnormalities that represent a worsening from baseline observed in antiretroviral treatment-experienced adult subjects treated with PREZISTA/ritonavir 600/100 mg twice daily are presented in Table 8.

Table 8: Grade 2 to 4 Laboratory Abnormalities Observed in Antiretroviral Treatment-Experienced HIV-1-Infected Adult Subjects [Grade 4 data not applicable in Division of AIDS grading scale]
 |  | Randomized Study TMC114-C214
Laboratory Parameter Preferred Term, % | Limit | PREZISTA/ritonavir 600/100 mg twice daily + OBR | lopinavir/ritonavir 400/100 mg twice daily + OBR
Biochemistry
Alanine Aminotransferase
Grade 2 | > 2.5 to ≤ 5.0 × ULN | 7% | 5%
Grade 3 | > 5.0 to ≤ 10.0 × ULN | 2% | 2%
Grade 4 | > 10.0 × ULN | 1% | 2%
Aspartate Aminotransferase
Grade 2 | > 2.5 to ≤ 5.0 × ULN | 6% | 6%
Grade 3 | > 5.0 to ≤ 10.0 × ULN | 2% | 2%
Grade 4 | > 10.0 × ULN | < 1% | 2%
Alkaline Phosphatase
Grade 2 | > 2.5 to ≤ 5.0 × ULN | < 1% | 0%
Grade 3 | > 5.0 to ≤ 10.0 × ULN | < 1% | < 1%
Grade 4 | > 10.0 × ULN | 0% | 0%
Hyperbilirubinemia
Grade 2 | > 1.5 to ≤ 2.5 × ULN | < 1% | 2%
Grade 3 | > 2.5 to ≤ 5.0 × ULN | < 1% | < 1%
Grade 4 | > 5.0 × ULN | < 1% | 0%
Triglycerides
Grade 2 | 5.65–8.48 mmol/L 500–750 mg/dL | 10% | 11%
Grade 3 | 8.49–13.56 mmol/L 751–1200 mg/dL | 7% | 10%
Grade 4 | > 13.56 mmol/L > 1200 mg/dL | 3% | 6%
Total Cholesterol
Grade 2 | 6.20–7.77 mmol/L 240–300 mg/dL | 25% | 23%
Grade 3 | > 7.77 mmol/L > 300 mg/dL | 10% | 14%
Low-Density Lipoprotein Cholesterol
Grade 2 | 4.13–4.90 mmol/L 160–190 mg/dL | 14% | 14%
Grade 3 | ≥ 4.91 mmol/L ≥ 191 mg/dL | 8% | 9%
Elevated Glucose Levels
Grade 2 | 6.95–13.88 mmol/L 126–250 mg/dL | 10% | 11%
Grade 3 | 13.89–27.75 mmol/L 251–500 mg/dL | 1% | < 1%
Grade 4 | > 27.75 mmol/L > 500 mg/dL | < 1% | 0%
Pancreatic Lipase
Grade 2 | > 1.5 to ≤ 3.0 × ULN | 3% | 4%
Grade 3 | > 3.0 to ≤ 5.0 × ULN | 2% | < 1%
Grade 4 | > 5.0 × ULN | < 1% | 0%
Pancreatic Amylase
Grade 2 | > 1.5 to ≤ 2.0 × ULN | 6% | 7%
Grade 3 | > 2.0 to ≤ 5.0 × ULN | 7% | 3%
Grade 4 | > 5.0 × ULN | 0% | 0%
N=total number of subjects per treatment group
OBR = optimized background regimen

6.3 Serious ADRs

The following serious ADRs of at least moderate intensity (greater than or equal to Grade 2) occurred in the Phase 2b studies and Phase 3 studies with PREZISTA/ritonavir: abdominal pain, acute hepatitis, acute pancreatitis, anorexia, asthenia, diabetes mellitus, diarrhea, fatigue, headache, hepatic enzyme increased, hypercholesterolemia, hyperglycemia, hypertriglyceridemia, immune reconstitution syndrome, low density lipoprotein increased, nausea, pancreatic enzyme increased, rash, Stevens-Johnson Syndrome, and vomiting.

6.4 Patients co-infected with hepatitis B and/or hepatitis C virus

In subjects co-infected with hepatitis B or C virus receiving PREZISTA/ritonavir, the incidence of adverse events and clinical chemistry abnormalities was not higher than in subjects receiving PREZISTA/ritonavir who were not co-infected, except for increased hepatic enzymes [see Warnings and Precautions (5.2)]. The pharmacokinetic exposure in co-infected subjects was comparable to that in subjects without co-infection.

6.5 Clinical Trials Experience: Pediatric Patients

PREZISTA/ritonavir has been studied in combination with other antiretroviral agents in 2 Phase II trials. TMC114-C212, in which 80 antiretroviral treatment-experienced HIV-1-infected pediatric subjects 6 to less than 18 years of age and weighing at least 20 kg were included and TMC114-C228, in which 21 antiretroviral treatment-experienced HIV-1-infected pediatric subjects 3 to less than 6 years of age and weighing at least 10 kg were included [see Use in Specific Populations (8.4) and Clinical Studies (14.4)].

Frequency, type, and severity of ADRs in pediatric subjects were comparable to those observed in adults.

Study TMC114-C212

ADRs to PREZISTA/ritonavir (all grades, greater than or equal to 3%), excluding laboratory abnormalities reported as ADRs, were vomiting (13%), diarrhea (11%), abdominal pain (10%), headache (9%), rash (5%), nausea (4%) and fatigue (3%).

Grade 3 or 4 laboratory abnormalities were ALT increased (Grade 3: 3%; Grade 4: 1%), AST increased (Grade 3: 1%), pancreatic amylase increased (Grade 3: 4%, Grade 4: 1%), pancreatic lipase increased (Grade 3: 1%), total cholesterol increased (Grade 3: 1%), and LDL increased (Grade 3: 3%).

Study TMC114-C228

ADRs to PREZISTA/ritonavir (all grades, greater than or equal to 3%), excluding laboratory abnormalities, were diarrhea (19%), vomiting (14%) and rash (10%).

There were no Grade 3 or 4 laboratory abnormalities considered as ADRs in this study.

6.6 Postmarketing Experience

The following events have been identified during postmarketing use of PREZISTA. Because these events are reported voluntarily from a population of unknown size, it is not always possible to reliably estimate their frequency or establish a causal relationship to drug exposure.

Redistribution of body fat has been reported.

Rarely, rhabdomyolysis (associated with co-administration with HMG-CoA reductase inhibitors and PREZISTA/ritonavir) has been reported.

In addition, toxic epidermal necrolysis and acute generalized exanthematous pustulosis have been reported rarely [see Warnings and Precautions (5.3)].

7 DRUG INTERACTIONS

See also Contraindications (4) and Clinical Pharmacology (12.3).

7.1 Potential for PREZISTA/ritonavir to Affect Other Drugs

PREZISTA co-administered with ritonavir is an inhibitor of CYP3A and CYP2D6. Co-administration of PREZISTA and ritonavir with drugs that are primarily metabolized by CYP3A and CYP2D6 may result in increased plasma concentrations of such drugs, which could increase or prolong their therapeutic effect and adverse events (see Table 9).

7.2 Potential for Other Drugs to Affect Darunavir

Darunavir and ritonavir are metabolized by CYP3A. Drugs that induce CYP3A activity would be expected to increase the clearance of darunavir and ritonavir, resulting in lowered plasma concentrations of darunavir and ritonavir. Co-administration of darunavir and ritonavir and other drugs that inhibit CYP3A may decrease the clearance of darunavir and ritonavir and may result in increased plasma concentrations of darunavir and ritonavir (see Table 9).

7.3 Established and Other Potentially Significant Drug Interactions

Table 9 provides dosing recommendations as a result of drug interactions with PREZISTA/ritonavir. These recommendations are based on either drug interaction studies or predicted interactions due to the expected magnitude of interaction and potential for serious adverse events or loss of efficacy.

Table 9: Established and Other Potentially Significant Drug Interactions: Alterations in Dose or Regimen May Be Recommended Based on Drug Interaction Studies or Predicted Interaction [See Clinical Pharmacology (12.3) for Magnitude of Interaction, Tables 12 and 13]
Concomitant Drug Class: Drug Name | Effect on Concentration of Darunavir or Concomitant Drug | Clinical Comment
HIV-1-Antiviral Agents: Nucleoside Reverse Transcriptase Inhibitors (NRTIs)
didanosine | ↔ darunavir ↔ didanosine | Didanosine should be administered one hour before or two hours after PREZISTA/ritonavir (which are administered with food).
HIV-1-Antiviral Agents: HIV-Protease Inhibitors (PIs)
indinavir (The reference regimen for indinavir was indinavir/ritonavir 800/100 mg twice daily.) | ↑ darunavir ↑ indinavir | The appropriate dose of indinavir in combination with PREZISTA/ritonavir has not been established.
lopinavir/ritonavir | ↓ darunavir ↔ lopinavir | Appropriate doses of the combination have not been established. Hence, it is not recommended to co-administer lopinavir/ritonavir and PREZISTA, with or without ritonavir.
saquinavir | ↓ darunavir ↔ saquinavir | Appropriate doses of the combination have not been established. Hence, it is not recommended to co-administer saquinavir and PREZISTA, with or without ritonavir.
HIV-1-Antiviral Agents: CCR5 co-receptor antagonists
maraviroc | ↑ maraviroc | Maraviroc concentrations are increased when co-administered with PREZISTA/ritonavir. When used in combination with PREZISTA/ritonavir, the dose of maraviroc should be 150 mg twice daily.
Other Agents
Antiarrhythmics: bepridil, lidocaine (systemic), quinidine, amiodarone, flecainide, propafenone | ↑ antiarrhythmics | Concentrations of these drugs may be increased when co-administered with PREZISTA/ritonavir. Caution is warranted and therapeutic concentration monitoring, if available, is recommended for antiarrhythmics when co-administered with PREZISTA/ritonavir.
digoxin | ↑ digoxin | The lowest dose of digoxin should initially be prescribed. The serum digoxin concentrations should be monitored and used for titration of digoxin dose to obtain the desired clinical effect.
Anticoagulant: warfarin | ↓ warfarin ↔ darunavir | Warfarin concentrations are decreased when co-administered with PREZISTA/ritonavir. It is recommended that the international normalized ratio (INR) be monitored when warfarin is combined with PREZISTA/ritonavir.
Anticonvulsant: carbamazepine | ↔ darunavir ↑ carbamazepine | The dose of either darunavir/ritonavir or carbamazepine does not need to be adjusted when initiating co-administration with darunavir/ritonavir and carbamazepine. Clinical monitoring of carbamazepine concentrations and its dose titration is recommended to achieve the desired clinical response.
Anticonvulsant: phenobarbital, phenytoin | ↔ darunavir ↓ phenytoin ↓ phenobarbital | Co-administration of PREZISTA/ritonavir may cause a decrease in the steady-state concentrations of phenytoin and phenobarbital. Phenytoin and phenobarbital levels should be monitored when co-administering with PREZISTA/ritonavir.
Antidepressant: trazodone, desipramine | ↑ trazodone ↑ desipramine | Concomitant use of trazodone or desipramine and PREZISTA/ritonavir may increase plasma concentrations of trazodone or desipramine which may lead to adverse events such as nausea, dizziness, hypotension and syncope. If trazodone or desipramine is used with PREZISTA/ritonavir, the combination should be used with caution, and a lower dose of trazodone or desipramine should be considered.
Anti-infective: clarithromycin | ↔ darunavir ↑ clarithromycin | No dose adjustment of the combination is required for patients with normal renal function. For patients with renal impairment, the following dose adjustments should be considered:; - For subjects with CLcr of 30–60 mL/min, the dose of clarithromycin should be reduced by 50%. - For subjects with CLcr of < 30 mL/min, the dose of clarithromycin should be reduced by 75%.
Antifungals: ketoconazole, itraconazole, voriconazole | ↑ ketoconazole ↑ darunavir ↑ itraconazole (not studied) ↓ voriconazole (not studied) | Ketoconazole and itraconazole are potent inhibitors as well as substrates of CYP3A. Concomitant systemic use of ketoconazole, itraconazole, and darunavir/ritonavir may increase plasma concentration of darunavir.
 |  | Plasma concentrations of ketoconazole or itraconazole may be increased in the presence of darunavir/ritonavir. When co-administration is required, the daily dose of ketoconazole or itraconazole should not exceed 200 mg.
 |  | Plasma concentrations of voriconazole may be decreased in the presence of darunavir/ritonavir. Voriconazole should not be administered to patients receiving darunavir/ritonavir unless an assessment of the benefit/risk ratio justifies the use of voriconazole.
Anti-gout: colchicine | ↑ colchicine | Treatment of gout-flares – co-administration of colchicine in patients on PREZISTA/ritonavir: 0.6 mg (1 tablet) × 1 dose, followed by 0.3 mg (half tablet) 1 hour later. Treatment course to be repeated no earlier than 3 days.; Prophylaxis of gout-flares – co-administration of colchicine in patients on PREZISTA/ritonavir: If the original regimen was 0.6 mg twice a day, the regimen should be adjusted to 0.3 mg once a day. If the original regimen was 0.6 mg once a day, the regimen should be adjusted to 0.3 mg once every other day.; Treatment of familial Mediterranean fever – co-administration of colchicine in patients on PREZISTA/ritonavir: maximum daily dose of 0.6 mg (may be given as 0.3 mg twice a day). Patients with renal or hepatic impairment should not be given colchicine with PREZISTA/ritonavir.
Antimycobacterial: rifabutin | ↑ darunavir ↑ rifabutin ↑ 25-O-desacetylrifabutin | Dose reduction of rifabutin by at least 75% of the usual dose (300 mg once daily) is recommended (i.e., a maximum dose of 150 mg every other day). Increased monitoring for adverse events is warranted in patients receiving this combination and further dose reduction of rifabutin may be necessary.
The reference regimen for rifabutin was 300 mg once daily | ↑ darunavir ↑ rifabutin ↑ 25-O-desacetylrifabutin | Dose reduction of rifabutin by at least 75% of the usual dose (300 mg once daily) is recommended (i.e., a maximum dose of 150 mg every other day). Increased monitoring for adverse events is warranted in patients receiving this combination and further dose reduction of rifabutin may be necessary.
β-Blockers: metoprolol, timolol | ↑ beta-blockers | Caution is warranted and clinical monitoring of patients is recommended. A dose decrease may be needed for these drugs when co-administered with PREZISTA/ritonavir.
Benzodiazepines: parenterally administered midazolam | ↑ midazolam | Concomitant use of parenteral midazolam with PREZISTA/ritonavir may increase plasma concentrations of midazolam. Co-administration should be done in a setting which ensures close clinical monitoring and appropriate medical management in case of respiratory depression and/or prolonged sedation. Dosage reduction for midazolam should be considered, especially if more than a single dose of midazolam is administered. Co-administration of oral midazolam with PREZISTA/ritonavir is CONTRAINDICATED.
Calcium Channel Blockers: felodipine, nifedipine, nicardipine | ↑ calcium channel blockers | Plasma concentrations of calcium channel blockers (e.g., felodipine, nifedipine, nicardipine) may increase when PREZISTA/ritonavir are co-administered. Caution is warranted and clinical monitoring of patients is recommended.
Corticosteroid: Systemic: dexamethasone | ↓ darunavir | Systemic dexamethasone induces CYP3A and can thereby decrease darunavir plasma concentrations. This may result in loss of therapeutic effect to PREZISTA.
Corticosteroid: Inhaled/Nasal: fluticasone | ↑ fluticasone | Concomitant use of inhaled fluticasone and PREZISTA/ritonavir may increase plasma concentrations of fluticasone. Alternatives should be considered, particularly for long-term use.
Endothelin receptor antagonists: bosentan | ↑ bosentan | Co-administration of bosentan in patients on PREZISTA/ritonavir: In patients who have been receiving PREZISTA/ritonavir for at least 10 days, start bosentan at 62.5 mg once daily or every other day based upon individual tolerability.; Co-administration of PREZISTA/ritonavir in patients on bosentan: Discontinue use of bosentan at least 36 hours prior to initiation of PREZISTA/ritonavir. After at least 10 days following the initiation of PREZISTA/ritonavir, resume bosentan at 62.5 mg once daily or every other day based upon individual tolerability.
Hepatitis C Virus (HCV) Direct-Acting Agents: NS3-4A protease inhibitors: boceprevir telaprevir | ↓ darunavir ↓ boceprevir ↓ telaprevir | Concomitant administration of PREZISTA/ritonavir and boceprevir or telaprevir resulted in reduced steady-state exposures to darunavir and boceprevir or telaprevir. It is not recommended to co-administer boceprevir or telaprevir and PREZISTA/ritonavir.
HMG-CoA Reductase Inhibitors: pravastatin, atorvastatin, rosuvastatin | ↑ pravastatin ↑ atorvastatin ↑ rosuvastatin | Titrate atorvastatin, pravastatin or rosuvastatin dose carefully and use the lowest necessary dose while monitoring for safety. Do not exceed atorvastatin 20 mg/day.
Immunosuppressants: cyclosporine, tacrolimus, sirolimus | ↑ immunosuppressants | Plasma concentrations of cyclosporine, tacrolimus or sirolimus may be increased when co-administered with PREZISTA/ritonavir. Therapeutic concentration monitoring of the immunosuppressive agent is recommended when co-administered with PREZISTA/ritonavir.
Inhaled beta agonist: salmeterol | ↑ salmeterol | Concurrent administration of salmeterol and PREZISTA/ritonavir is not recommended. The combination may result in increased risk of cardiovascular adverse events associated with salmeterol, including QT prolongation, palpitations and sinus tachycardia.
Narcotic Analgesic/Treatment of Opioid Dependence: methadone, buprenorphine, buprenorphine/naloxone | ↓ methadone ↔ buprenorphine, naloxone ↑ norbuprenorphine (metabolite) | No adjustment of methadone dosage is required when initiating co-administration of PREZISTA/ritonavir. However, clinical monitoring is recommended as the dose of methadone during maintenance therapy may need to be adjusted in some patients. No dose adjustment for buprenorphine or buprenorphine/naloxone is required with concurrent administration of PREZISTA/ritonavir. Clinical monitoring is recommended if PREZISTA/ritonavir and buprenorphine or buprenorphine/naloxone are coadministered.
Neuroleptics: risperidone, thioridazine | ↑ neuroleptics | A dose decrease may be needed for these drugs when co-administered with PREZISTA/ritonavir.
Oral Contraceptives/estrogen: ethinyl estradiol, norethindrone | ↓ ethinyl estradiol ↓ norethindrone | Plasma concentrations of ethinyl estradiol are decreased due to induction of its metabolism by ritonavir. Alternative methods of nonhormonal contraception are recommended.
PDE-5 inhibitors: sildenafil, vardenafil, tadalafil | ↑ PDE-5 inhibitors (only the use of sildenafil at doses used for treatment of erectile dysfunction has been studied with PREZISTA/ritonavir) | Co-administration with PREZISTA/ritonavir may result in an increase in PDE-5 inhibitor-associated adverse events, including hypotension, syncope, visual disturbances and priapism.; Use of PDE-5 inhibitors for pulmonary arterial hypertension (PAH):; - Use of sildenafil is contraindicated when used for the treatment of pulmonary arterial hypertension (PAH) [see Contraindications (4)]. - The following dose adjustments are recommended for use of tadalafil with PREZISTA/ritonavir: Co-administration of tadalafil in patients on PREZISTA/ritonavir: In patients receiving PREZISTA/ritonavir for at least one week, start tadalafil at 20 mg once daily. Increase to 40 mg once daily based upon individual tolerability. Co-administration of PREZISTA/ritonavir in patients on tadalafil: Avoid use of tadalafil during the initiation of PREZISTA/ritonavir. Stop tadalafil at least 24 hours prior to starting PREZISTA/ritonavir. After at least one week following the initiation of PREZISTA/ritonavir, resume tadalafil at 20 mg once daily. Increase to 40 mg once daily based upon individual tolerability.; Use of PDE-5 inhibitors for erectile dysfunction: Sildenafil at a single dose not exceeding 25 mg in 48 hours, vardenafil at a single dose not exceeding 2.5 mg dose in 72 hours, or tadalafil at a single dose not exceeding 10 mg dose in 72 hours can be used with increased monitoring for PDE-5 inhibitor-associated adverse events.
Selective Serotonin Reuptake Inhibitors (SSRIs): sertraline, paroxetine | ↔ darunavir ↓ sertraline ↓ paroxetine | If sertraline or paroxetine is co-administered with PREZISTA/ritonavir, the recommended approach is a careful dose titration of the SSRI based on a clinical assessment of antidepressant response. In addition, patients on a stable dose of sertraline or paroxetine who start treatment with PREZISTA/ritonavir should be monitored for antidepressant response.

In addition to the drugs included in Table 9, the interaction between PREZISTA/ritonavir and the following drugs were evaluated in clinical studies and no dose adjustments are needed for either drug [see Clinical Pharmacology (12.3)]: atazanavir, efavirenz, etravirine, nevirapine, omeprazole, ranitidine, rilpivirine, and tenofovir disoproxil fumarate.

Other nucleoside reverse transcriptase inhibitors (NRTIs):

Based on the different elimination pathways of the other NRTIs (zidovudine, zalcitabine, emtricitabine, stavudine, lamivudine and abacavir) that are primarily renally excreted, no drug interactions are expected for these drugs and PREZISTA/ritonavir.

Other PIs:

The co-administration of PREZISTA/ritonavir and PIs other than lopinavir/ritonavir, saquinavir, atazanavir, and indinavir has not been studied. Therefore, such co-administration is not recommended.

8 USE IN SPECIFIC POPULATIONS

8.1 Pregnancy

TERATOGENIC EFFECTS

Pregnancy Category C: PREZISTA should be used during pregnancy only if the potential benefit justifies the potential risk.

No adequate and well-controlled studies have been conducted in pregnant women. Reproduction studies conducted with darunavir showed no embryotoxicity or teratogenicity in mice and rats in the presence or absence of ritonavir as well as in rabbits with darunavir alone. In these studies, darunavir exposures (based on AUC) were higher in rats (3-fold), whereas in mice and rabbits, exposures were lower (less than 1-fold) compared to those obtained in humans at the recommended clinical dose of darunavir boosted with ritonavir.

In the rat pre- and postnatal development study, a reduction in pup body weight gain was observed with darunavir alone or in combination with ritonavir during lactation. This was due to exposure of pups to drug substances via the milk. Sexual development, fertility and mating performance of offspring were not affected by maternal treatment with darunavir alone or in combination with ritonavir. The maximal plasma exposures achieved in rats were approximately 50% of those obtained in humans at the recommended clinical dose boosted with ritonavir.

In the juvenile toxicity study where rats were directly dosed with darunavir, deaths occurred from post-natal day 5 through 11 at plasma exposure levels ranging from 0.1 to 1.0 of the human exposure levels. In a 4-week rat toxicology study, when dosing was initiated on post-natal day 23 (the human equivalent of 2 to 3 years of age), no deaths were observed with a plasma exposure (in combination with ritonavir) of 0.1 of the human plasma exposure levels.

Antiretroviral Pregnancy Registry: To monitor maternal-fetal outcomes of pregnant women exposed to PREZISTA, an Antiretroviral Pregnancy Registry has been established. Physicians are encouraged to register patients by calling 1-800-258-4263.

8.3 Nursing Mothers

The Centers for Disease Control and Prevention recommend that HIV-infected mothers in the United States not breastfeed their infants to avoid risking postnatal transmission of HIV. Although it is not known whether darunavir is secreted in human milk, darunavir is secreted into the milk of lactating rats. Because of both the potential for HIV transmission and the potential for serious adverse reactions in nursing infants, mothers should be instructed not to breastfeed if they are receiving PREZISTA.

8.4 Pediatric Use

Do not administer PREZISTA/ritonavir in pediatric patients below 3 years of age because of toxicity and mortality observed in juvenile rats dosed with darunavir (from 20 mg/kg to 1000 mg/kg) up to days 23 to 26 of age [see Warnings and Precautions (5.11), Use in Specific Populations (8.1), Clinical Pharmacology (12.3) and Nonclinical Toxicology (13.2)].

Do not administer PREZISTA/ritonavir once daily in pediatric patients.

The safety, pharmacokinetic profile, and virologic and immunologic responses of PREZISTA/ritonavir were evaluated in treatment-experienced HIV-1-infected pediatric subjects 3 to less than 18 years of age and weighing at least 10 kg [see Adverse Reactions (6.6), Clinical Pharmacology (12.3) and Clinical Studies (14.4)]. Frequency, type, and severity of adverse drug reactions in pediatric subjects were comparable to those observed in adults [see Adverse Reactions (6.6)]. Please see Dosage and Administration (2.2) for dosing recommendations for pediatric subjects 3 to less than 18 years of age and weighing at least 10 kg.

8.5 Geriatric Use

Clinical studies of PREZISTA did not include sufficient numbers of patients aged 65 and over to determine whether they respond differently from younger patients. In general, caution should be exercised in the administration and monitoring of PREZISTA in elderly patients, reflecting the greater frequency of decreased hepatic function, and of concomitant disease or other drug therapy [see Clinical Pharmacology (12.3)].

8.6 Hepatic Impairment

No dose adjustment of PREZISTA/ritonavir is necessary for patients with either mild or moderate hepatic impairment. No pharmacokinetic or safety data are available regarding the use of PREZISTA/ritonavir in subjects with severe hepatic impairment. Therefore, PREZISTA/ritonavir is not recommended for use in patients with severe hepatic impairment [see Dosage and Administration (2.3) and Clinical Pharmacology (12.3)].

8.7 Renal Impairment

Population pharmacokinetic analysis showed that the pharmacokinetics of darunavir were not significantly affected in HIV-infected subjects with moderate renal impairment (CrCL between 30–60 mL/min, n=20). No pharmacokinetic data are available in HIV-1-infected patients with severe renal impairment or end stage renal disease; however, because the renal clearance of darunavir is limited, a decrease in total body clearance is not expected in patients with renal impairment. As darunavir and ritonavir are highly bound to plasma proteins, it is unlikely that they will be significantly removed by hemodialysis or peritoneal dialysis [see Clinical Pharmacology (12.3)].

10 OVERDOSAGE

Human experience of acute overdose with PREZISTA/ritonavir is limited. Single doses up to 3200 mg of the oral solution of darunavir alone and up to 1600 mg of the tablet formulation of darunavir in combination with ritonavir have been administered to healthy volunteers without untoward symptomatic effects.

No specific antidote is available for overdose with PREZISTA. Treatment of overdose with PREZISTA consists of general supportive measures including monitoring of vital signs and observation of the clinical status of the patient. If indicated, elimination of unabsorbed active substance is to be achieved by emesis or gastric lavage. Administration of activated charcoal may also be used to aid in removal of unabsorbed active substance. Since PREZISTA is highly protein bound, dialysis is unlikely to be beneficial in significant removal of the active substance.

11 DESCRIPTION

PREZISTA (darunavir) is an inhibitor of the human immunodeficiency virus (HIV-1) protease.

PREZISTA (darunavir), in the form of darunavir ethanolate, has the following chemical name: [(1S,2R)-3-[[(4-aminophenyl)sulfonyl](2-methylpropyl)amino]-2-hydroxy-1-(phenylmethyl)propyl]-carbamic acid (3R,3aS,6aR)-hexahydrofuro[2,3-b]furan-3-yl ester monoethanolate. Its molecular formula is C27H37N3O7S • C2H5OH and its molecular weight is 593.73. Darunavir ethanolate has the following structural formula:

Darunavir ethanolate is a white to off-white powder with a solubility of approximately 0.15 mg/mL in water at 20°C.

PREZISTA 100 mg/mL oral suspension is available as a white to off-white opaque suspension for oral administration.

PREZISTA 75 mg tablets are available as white, caplet-shaped, film-coated tablets for oral administration. PREZISTA 150 mg tablets are available as white, oval-shaped, film-coated tablets for oral administration. PREZISTA 600 mg tablets are available as orange, oval-shaped, film-coated tablets for oral administration. PREZISTA 400 mg tablets are available as light orange, oval-shaped, film-coated tablets for oral administration.

Each mL of the oral suspension contains darunavir ethanolate equivalent to 100 mg darunavir. In addition, each mL contains the inactive ingredients hydroxypropyl cellulose, microcrystalline cellulose, sodium carboxymethylcellulose, methylparaben sodium, citric acid monohydrate, sucralose, masking flavor, strawberry cream flavor, hydrochloric acid (for pH adjustment) and purified water.

Each 75 mg tablet contains darunavir ethanolate equivalent to 75 mg of darunavir. Each 150 mg tablet contains darunavir ethanolate equivalent to 150 mg of darunavir. Each 400 mg tablet contains darunavir ethanolate equivalent to 400 mg of darunavir. Each 600 mg tablet contains darunavir ethanolate equivalent to 600 mg of darunavir. During storage, partial conversion from ethanolate to hydrate may occur; however, this does not affect product quality or performance. Each tablet also contains the inactive ingredients colloidal silicon dioxide, crospovidone, magnesium stearate, and microcrystalline cellulose. The tablet film coating, OPADRY® White, contains polyethylene glycol 3350, polyvinyl alcohol-partially hydrolyzed, talc, and titanium dioxide. The tablet film coating, OPADRY® Orange, contains FD&C Yellow No. 6, polyethylene glycol 3350, polyvinyl alcohol-partially hydrolyzed, talc, and titanium dioxide.

All dosages for PREZISTA are expressed in terms of the free form of darunavir.

12 CLINICAL PHARMACOLOGY

12.1 Mechanism of Action

Darunavir is an HIV-1 antiviral drug [see Clinical Pharmacology (12.4)].

12.2 Pharmacodynamics

In an open-label, randomized, placebo- and active-controlled, four-way crossover trial, 40 healthy subjects were administered supratheraputic doses of darunavir/ritonavir 1600/100 mg once daily and 800/100 mg twice daily for seven days.

At the mean maximum darunavir concentration of 6599 ng/mL observed in this study, the mean increase in QTcF was 2.2 ms with a 90% two-sided confidence interval (CI) of -2.0 to 6.3 ms. When evaluating the 2-sided 90% CI on the time-matched mean changes in QTcF versus placebo control, the upper bounds of both darunavir/ritonavir groups never exceeded the 10 ms boundary. In the setting of this trial, darunavir/ritonavir did not appear to prolong the QTc interval.

12.3 Pharmacokinetics

Pharmacokinetics in Adults

General

Darunavir is primarily metabolized by CYP3A. Ritonavir inhibits CYP3A, thereby increasing the plasma concentrations of darunavir. When a single dose of PREZISTA 600 mg was given orally in combination with 100 mg ritonavir twice daily, there was an approximate 14-fold increase in the systemic exposure of darunavir. Therefore, PREZISTA should only be used in combination with 100 mg of ritonavir to achieve sufficient exposures of darunavir.

The pharmacokinetics of darunavir, co-administered with low dose ritonavir (100 mg), has been evaluated in healthy adult volunteers and in HIV-1-infected subjects. Table 10 displays the population pharmacokinetic estimates of darunavir after oral administration of PREZISTA/ritonavir 600/100 mg twice daily [based on sparse sampling in 285 patients in study TMC114-C214, 278 patients in Study TMC114-C229 and 119 patients (integrated data) from Studies TMC114-C202 and TMC114-C213] and PREZISTA/ritonavir 800/100 mg once daily [based on sparse sampling in 335 patients in Study TMC114-C211 and 280 patients in Study TMC114-C229] to HIV-1-infected patients.

Table 10: Population Pharmacokinetic Estimates of Darunavir at PREZISTA/ritonavir 800/100 mg Once Daily (Study TMC114-C211, 48-Week Analysis and Study TMC114-C229, 48-Week Analysis) and PREZISTA/ritonavir 600/100 mg Twice Daily (Study TMC114-C214, 48-Week Analysis, Study TMC114-C229, 48-Week Analysis and Integrated data from Studies TMC114-C213 and TMC114-C202, Primary 24-Week Analysis)
Parameter | Study TMC114-C211 PREZISTA/ ritonavir 800/100 mg once daily N = 335 | Study TMC114-C229 PREZISTA/ ritonavir 800/100 mg once daily N = 280 | Study TMC114-C214 PREZISTA/ ritonavir 600/100 mg twice daily N = 285 | Study TMC114-C229 PREZISTA/ ritonavir 600/100 mg twice daily N = 278 | Studies TMC114-C213 and TMC114-C202 (integrated data) PREZISTA/ ritonavir 600/100 mg twice daily N =119
AUC24h (ng∙h/mL) [AUC24h is calculated as AUC12h*2]
Mean ± Standard Deviation | 93026 ± 27050 | 93334 ± 28626 | 116796 ± 33594 | 114302 ± 32681 | 124698 ± 32286
Median (Range) | 87854 (45000–219240) | 87788 (45456–236920) | 111632 (64874–355360) | 109401 (48934–323820) | 123336 (67714–212980)
C0h (ng/mL)
Mean ± Standard Deviation | 2282 ± 1168 | 2160 ± 1201 | 3490 ± 1401 | 3386 ± 1372 | 3578 ± 1151
Median (Range) | 2041 (368–7242) | 1896 (184–7881) | 3307 (1517–13198) | 3197 (250–11865) | 3539 (1255–7368)
N = number of subjects with data

Absorption and Bioavailability

Darunavir, co-administered with 100 mg ritonavir twice daily, was absorbed following oral administration with a Tmax of approximately 2.5–4 hours. The absolute oral bioavailability of a single 600 mg dose of darunavir alone and after co-administration with 100 mg ritonavir twice daily was 37% and 82%, respectively. In vivo data suggest that darunavir/ritonavir is an inhibitor of the p-glycoprotein (p-gp) transporters.

Effects of Food on Oral Absorption

When PREZISTA tablets were administered with food, the Cmax and AUC of darunavir, co-administered with ritonavir, is approximately 40% higher relative to the fasting state. Therefore, PREZISTA tablets, co-administered with ritonavir, should always be taken with food. Within the range of meals studied, darunavir exposure is similar. The total caloric content of the various meals evaluated ranged from 240 Kcal (12 gms fat) to 928 Kcal (56 gms fat).

Distribution

Darunavir is approximately 95% bound to plasma proteins. Darunavir binds primarily to plasma alpha 1-acid glycoprotein (AAG).

Metabolism

In vitro experiments with human liver microsomes (HLMs) indicate that darunavir primarily undergoes oxidative metabolism. Darunavir is extensively metabolized by CYP enzymes, primarily by CYP3A. A mass balance study in healthy volunteers showed that after a single dose administration of 400 mg ^14C-darunavir, co-administered with 100 mg ritonavir, the majority of the radioactivity in the plasma was due to darunavir. At least 3 oxidative metabolites of darunavir have been identified in humans; all showed activity that was at least 90% less than the activity of darunavir against wild-type HIV-1.

Elimination

A mass balance study in healthy volunteers showed that after single dose administration of 400 mg ^1^4C-darunavir, co-administered with 100 mg ritonavir, approximately 79.5% and 13.9% of the administered dose of ^1^4C-darunavir was recovered in the feces and urine, respectively. Unchanged darunavir accounted for approximately 41.2% and 7.7% of the administered dose in feces and urine, respectively. The terminal elimination half-life of darunavir was approximately 15 hours when co-administered with ritonavir. After intravenous administration, the clearance of darunavir, administered alone and co-administered with 100 mg twice daily ritonavir, was 32.8 L/h and 5.9 L/h, respectively.

Special Populations

Hepatic Impairment

Darunavir is primarily metabolized by the liver. The steady-state pharmacokinetic parameters of darunavir were similar after multiple dose co-administration of PREZISTA/ritonavir 600/100 mg twice daily to subjects with normal hepatic function (n=16), mild hepatic impairment (Child-Pugh Class A, n=8), and moderate hepatic impairment (Child-Pugh Class B, n=8). The effect of severe hepatic impairment on the pharmacokinetics of darunavir has not been evaluated [see Dosage and Administration (2.3) and Use in Specific Populations (8.6)].

Hepatitis B or Hepatitis C Virus Co-infection

The 48-week analysis of the data from Studies TMC114-C211 and TMC114-C214 in HIV-1-infected subjects indicated that hepatitis B and/or hepatitis C virus co-infection status had no apparent effect on the exposure of darunavir.

Renal Impairment

Results from a mass balance study with ^14C-darunavir/ritonavir showed that approximately 7.7% of the administered dose of darunavir is excreted in the urine as unchanged drug. As darunavir and ritonavir are highly bound to plasma proteins, it is unlikely that they will be significantly removed by hemodialysis or peritoneal dialysis. Population pharmacokinetic analysis showed that the pharmacokinetics of darunavir were not significantly affected in HIV-1-infected subjects with moderate renal impairment (CrCL between 30–60 mL/min, n=20). There are no pharmacokinetic data available in HIV-1-infected patients with severe renal impairment or end stage renal disease [see Use in Specific Populations (8.7)].

Gender

Population pharmacokinetic analysis showed higher mean darunavir exposure in HIV-1-infected females compared to males. This difference is not clinically relevant.

Race

Population pharmacokinetic analysis of darunavir in HIV-1-infected subjects indicated that race had no apparent effect on the exposure to darunavir.

Geriatric Patients

Population pharmacokinetic analysis in HIV-1-infected subjects showed that darunavir pharmacokinetics are not considerably different in the age range (18 to 75 years) evaluated in HIV-1-infected subjects (n = 12, age greater than or equal to 65) [see Use in Specific Populations (8.5)].

Pediatric Patients

The pharmacokinetics of darunavir in combination with ritonavir in 92 antiretroviral treatment-experienced HIV-1-infected pediatric subjects 3 to less than 18 years of age and weighing at least 10 kg showed that the administered weight-based dosages resulted in darunavir exposure that was comparable to the exposures achieved in treatment-experienced adults receiving PREZISTA/ritonavir 600/100 mg twice daily [see Dosage and Administration (2.2)].

Table 11: Population Pharmacokinetic Estimates of Darunavir Exposure (Study TMC114-C212 and Study TMC114-C228) Following Administration of Doses in Tables 1 and 2
Parameter | Study TMC114-C212 PREZISTA/ ritonavir twice daily N = 74 | Study TMC114-C228 PREZISTA/ ritonavir twice daily
Parameter | Study TMC114-C212 PREZISTA/ ritonavir twice daily N = 74 | 10 to less than 15 kg N = 10 | 15 to less than 20 kg N = 12
AUC24h (ng∙h/mL)
Mean ± Standard Deviation | 126377 (34356) | 137399 ± 51067 | 158773 ± 61932
Median (Range) | 127340 (67054–230720) | 123229 (92098–262720) | 138578 (104974–317420)
C0h (ng/mL)
Mean ± Standard Deviation | 3948 (1363) | 4429 ± 2064 | 4858 ± 2521
Median (Range) | 3888 (1836–7821) | 4010 (2576–9488) | 4469 (2733–11300)
N = number of subjects with data.

Drug Interactions

[See also Contraindications (4), Warnings and Precautions (5.5), and Drug Interactions (7).]

Darunavir co-administered with ritonavir is an inhibitor of CYP3A and CYP2D6. Co-administration of darunavir and ritonavir with drugs primarily metabolized by CYP3A and CYP2D6 may result in increased plasma concentrations of such drugs, which could increase or prolong their therapeutic effect and adverse events.

Darunavir and ritonavir are metabolized by CYP3A. Drugs that induce CYP3A activity would be expected to increase the clearance of darunavir and ritonavir, resulting in lowered plasma concentrations of darunavir and ritonavir. Co-administration of darunavir and ritonavir and other drugs that inhibit CYP3A may decrease the clearance of darunavir and ritonavir and may result in increased plasma concentrations of darunavir and ritonavir.

Drug interaction studies were performed with darunavir and other drugs likely to be co-administered and some drugs commonly used as probes for pharmacokinetic interactions. The effects of co-administration of darunavir on the AUC, Cmax, and Cmin values are summarized in Table 12 (effect of other drugs on darunavir) and Table 13 (effect of darunavir on other drugs). For information regarding clinical recommendations, see Drug Interactions (7).

Several interaction studies have been performed with a dose other than the recommended dose of the co-administered drug or darunavir; however, the results are applicable to the recommended dose of the co-administered drug and/or darunavir.

Table 12: Drug Interactions: Pharmacokinetic Parameters for Darunavir in the Presence of Co-administered Drugs
Co-Administered Drug | Dose/Schedule |  | N | PK | LS Mean Ratio (90% CI) of Darunavir Pharmacokinetic Parameters With/Without Co-administered Drug No Effect =1.00
Co-Administered Drug | Co-Administered Drug | Darunavir/ ritonavir | N | PK | Cmax | AUC | Cmin
Co-Administration With Other HIV Protease Inhibitors
Atazanavir | 300 mg q.d. [q.d. = once daily] | 400/100 mg b.i.d. [b.i.d. = twice daily] | 13 | ↔ | 1.02 (0.96–1.09) | 1.03 (0.94–1.12) | 1.01 (0.88–1.16)
Indinavir | 800 mg b.i.d. | 400/100 mg b.i.d. | 9 | ↑ | 1.11 (0.98–1.26) | 1.24 (1.09–1.42) | 1.44 (1.13–1.82)
Lopinavir/ Ritonavir | 400/100 mg b.i.d. | 1200/100 mg b.i.d. [The pharmacokinetic parameters of darunavir in this study were compared with the pharmacokinetic parameters following administration of darunavir/ritonavir 600/100 mg b.i.d.] | 14 | ↓ | 0.79 (0.67–0.92) | 0.62 (0.53–0.73) | 0.49 (0.39–0.63)
 | 533/133.3 mg b.i.d. | 1200 mg b.i.d. | 15 | ↓ | 0.79 (0.64–0.97) | 0.59 (0.50–0.70) | 0.45 (0.38–0.52)
Saquinavir hard gel capsule | 1000 mg b.i.d. | 400/100 mg b.i.d. | 14 | ↓ | 0.83 (0.75–0.92) | 0.74 (0.63–0.86) | 0.58 (0.47–0.72)
Co-Administration With Other HIV Antiretrovirals
Didanosine | 400 mg q.d. | 600/100 mg b.i.d. | 17 | ↔ | 0.93 (0.86–1.00) | 1.01 (0.95–1.07) | 1.07 (0.95–1.21)
Efavirenz | 600 mg q.d. | 300/100 mg b.i.d. | 12 | ↓ | 0.85 (0.72–1.00) | 0.87 (0.75–1.01) | 0.69 (0.54–0.87)
Etravirine | 200 mg b.i.d. | 600/100 mg b.i.d. | 15 | ↔ | 1.11 (1.01–1.22) | 1.15 (1.05–1.26) | 1.02 (0.90–1.17)
Nevirapine | 200 mg b.i.d. | 400/100 mg b.i.d. | 8 | ↑ | 1.40 [Ratio based on between-study comparison.] (1.14–1.73) | 1.24 (0.97–1.57) | 1.02 (0.79–1.32)
Rilpivirine | 150 mg q.d. | 800/100 mg q.d. | 15 | ↔ | 0.90 (0.81–1.00) | 0.89 (0.81–0.99) | 0.89 (0.68–1.16)
Tenofovir Disoproxil Fumarate | 300 mg q.d. | 300/100 mg b.i.d. | 12 | ↑ | 1.16 (0.94–1.42) | 1.21 (0.95–1.54) | 1.24 (0.90–1.69)
Co-Administration With HCV NS3-4A Protease Inhibitors
Boceprevir [AUC is AUC(0-last); N = 10 for Cmin in the reference arm] | 800 mg three times daily | 600/100 mg b.i.d. | 11 | ↓ | 0.64 (0.58–0.71) | 0.56 (0.51–0.61) | 0.41 (0.38–0.45)
Telaprevir | 750 mg every 8 hours 1125 mg every 12 hours | 600/100 mg b.i.d. 600/100 mg b.i.d. | 11 [N = 14 for Cmax] 15 | ↓ ↓ | 0.60 (0.56–0.64) 0.53 (0.47–0.59) | 0.60 (0.57–0.63) 0.49 (0.43–0.55) | 0.58 (0.52–0.64) 0.42 (0.35–0.51)
Co-Administration With Other Drugs
Carbamazepine | 200 mg b.i.d. | 600/100 mg b.i.d. | 16 | ↔ | 1.04 (0.93–1.16) | 0.99 (0.90–1.08) | 0.85 (0.73–1.00)
Clarithromycin | 500 mg b.i.d. | 400/100 mg b.i.d. | 17 | ↔ | 0.83 (0.72–0.96) | 0.87 (0.75–1.01) | 1.01 (0.81–1.26)
Ketoconazole | 200 mg b.i.d. | 400/100 mg b.i.d. | 14 | ↑ | 1.21 (1.04–1.40) | 1.42 (1.23–1.65) | 1.73 (1.39–2.14)
Omeprazole | 20 mg q.d. | 400/100 mg b.i.d. | 16 | ↔ | 1.02 (0.95–1.09) | 1.04 (0.96–1.13) | 1.08 (0.93–1.25)
Paroxetine | 20 mg q.d. | 400/100 mg b.i.d. | 16 | ↔ | 0.97 (0.92–1.02) | 1.02 (0.95–1.10) | 1.07 (0.96–1.19)
Ranitidine | 150 mg b.i.d. | 400/100 mg b.i.d. | 16 | ↔ | 0.96 (0.89–1.05) | 0.95 (0.90–1.01) | 0.94 (0.90–0.99)
Rifabutin | 150 mg q.o.d. [q.o.d. = every other day] | 600/100 mg b.i.d. | 11 | ↑ | 1.42 (1.21–1.67) | 1.57 (1.28–1.93) | 1.75 (1.28–2.37)
Sertraline | 50 mg q.d. | 400/100 mg b.i.d. | 13 | ↔ | 1.01 (0.89–1.14) | 0.98 (0.84–1.14) | 0.94 (0.76–1.16)
N = number of subjects with data

Table 13: Drug Interactions: Pharmacokinetic Parameters for Co-administered Drugs in the Presence of Darunavir/Ritonavir
Co-Administered Drug | Dose/Schedule |  | N | PK | LS Mean Ratio (90% CI) of Co-Administered Drug Pharmacokinetic Parameters With/Without Darunavir No effect =1.00
Co-Administered Drug | Co-Administered Drug | Darunavir/ ritonavir | N | PK | Cmax | AUC | Cmin
Co-Administration With Other HIV Protease Inhibitors
Atazanavir | 300 mg q.d. [q.d. = once daily] /100 mg ritonavir q.d. when administered alone | 400/100 mg b.i.d. [b.i.d. = twice daily] | 13 | ↔ | 0.89 (0.78–1.01) | 1.08 (0.94–1.24) | 1.52 (0.99–2.34)
 | 300 mg q.d. when administered with darunavir/ritonavir
Indinavir | 800 mg b.i.d. /100 mg ritonavir b.i.d. when administered alone | 400/100 mg b.i.d. | 9 | ↑ | 1.08 (0.95–1.22) | 1.23 (1.06–1.42) | 2.25 (1.63–3.10)
 | 800 mg b.i.d. when administered with darunavir/ ritonavir
Lopinavir/Ritonavir | 400/100 mg b.i.d. [The pharmacokinetic parameters of lopinavir in this study were compared with the pharmacokinetic parameters following administration of lopinavir/ritonavir 400/100 mg b.i.d.] | 1200/100 mg b.i.d. | 14 | ↔ | 0.98 (0.78–1.22) | 1.09 (0.86–1.37) | 1.23 (0.90–1.69)
 | 533/133.3 mg b.i.d. | 1200 mg b.i.d. | 15 | ↔ | 1.11 (0.96–1.30) | 1.09 (0.96–1.24) | 1.13 (0.90–1.42)
Saquinavir hard gel capsule | 1000 mg b.i.d. /100 mg ritonavir b.i.d. when administered alone | 400/100 mg b.i.d. | 12 | ↔ | 0.94 (0.78–1.13) | 0.94 (0.76–1.17) | 0.82 (0.52–1.30)
 | 1000 mg b.i.d. when administered with darunavir/ritonavir
Co-Administration With Other HIV Antiretrovirals
Didanosine | 400 mg q.d. | 600/100 mg b.i.d. | 17 | ↔ | 0.84 (0.59–1.20) | 0.91 (0.75–1.10) | -
Efavirenz | 600 mg q.d. | 300/100 mg b.i.d. | 12 | ↑ | 1.15 (0.97–1.35) | 1.21 (1.08–1.36) | 1.17 (1.01–1.36)
Etravirine | 100 mg b.i.d. | 600/100 mg b.i.d. | 14 | ↓ | 0.68 (0.57–0.82) | 0.63 (0.54–0.73) | 0.51 (0.44–0.61)
Nevirapine | 200 mg b.i.d. | 400/100 mg b.i.d. | 8 | ↑ | 1.18 (1.02–1.37) | 1.27 (1.12–1.44) | 1.47 (1.20–1.82)
Rilpivirine | 150 mg q.d. | 800/100 mg q.d. | 14 | ↑ | 1.79 (1.56–2.06) | 2.30 (1.98–2.67) | 2.78 (2.39–3.24)
Tenofovir Disoproxil Fumarate | 300 mg q.d. | 300/100 mg b.i.d. | 12 | ↑ | 1.24 (1.08–1.42) | 1.22 (1.10–1.35) | 1.37 (1.19–1.57)
Maraviroc | 150 mg b.i.d. | 600/100 mg b.i.d. | 12 | ↑ | 2.29 (1.46–3.59) | 4.05 (2.94–5.59) | 8.00 (6.35–10.1)
Maraviroc | 150 mg b.i.d. | 600/100 mg b.i.d. with 200 mg b.i.d. etravirine | 10 | ↑ | 1.77 (1.20–2.60) | 3.10 (2.57–3.74) | 5.27 (4.51–6.15)
Co-Administration With HCV NS3-4A Protease Inhibitors
Boceprevir | 800 mg three times daily | 600/100 mg b.i.d. | 12 [N = 11 for the test arm] | ↓ | 0.75 (0.67–0.85) | 0.68 (0.65–0.72) | 0.65 (0.56–0.76)
Telaprevir | 750 mg every 8 hours | 600/100 mg b.i.d. | 11 [N = 14 for Cmax] | ↓ | 0.64 (0.61–0.67) | 0.65 (0.61–0.69) | 0.68 (0.63–0.74)
Co-Administration With Other Drugs
Atorvastatin | 40 mg q.d. when administered alone | 300/100 mg b.i.d. | 15 | ↑ | 0.56 (0.48–0.67) | 0.85 (0.76–0.97) | 1.81 (1.37–2.40)
 | 10 mg q.d. when administered with darunavir/ritonavir
Buprenorphine/ Naloxone | 8/2 mg to 16/4 mg q.d. | 600/100 mg b.i.d. | 17 | ↔ | 0.92 [ratio is for buprenorphine; mean Cmax and AUC24 for naloxone were comparable when buprenorphine/naloxone was administered with or without PREZISTA/ritonavir] (0.79–1.08) | 0.89 (0.78–1.02) | 0.98 (0.82–1.16)
Norbuprenorphine |  |  | 17 | ↑ | 1.36 (1.06–1.74) | 1.46 (1.15–1.85) | 1.71 (1.29–2.27)
Carbamazepine | 200 mg b.i.d. | 600/100 mg b.i.d. | 16 | ↑ | 1.43 (1.34–1.53) | 1.45 (1.35–1.57) | 1.54 (1.41–1.68)
Carbamazepine epoxide |  |  | 16 | ↓ | 0.46 (0.43–0.49) | 0.46 (0.44–0.49) | 0.48 (0.45–0.51)
Clarithromycin | 500 mg b.i.d. | 400/100 mg b.i.d. | 17 | ↑ | 1.26 (1.03–1.54) | 1.57 (1.35–1.84) | 2.74 (2.30–3.26)
Dextromethorphan | 30 mg | 600/100 mg b.i.d. | 12 | ↑ | 2.27 (1.59–3.26) | 2.70 (1.80–4.05) | -
Dextrorphan |  |  |  | ↓ | 0.87 (0.77–0.98) | 0.96 (0.90–1.03) | -
Digoxin | 0.4 mg | 600/100 mg b.i.d. | 8 | ↑ | 1.15 (0.89–1.48) | 1.36 (0.81–2.27) | -
Ethinyl estradiol (EE) | Ortho-Novum 1/35 (35 µg EE / 1 mg NE) | 600/100 mg b.i.d. | 11 | ↓ | 0.68 (0.61–0.74) | 0.56 (0.50–0.63) | 0.38 (0.27–0.54)
Norethindrone (NE) |  |  | 11 | ↓ | 0.90 (0.83–0.97) | 0.86 (0.75–0.98) | 0.70 (0.51–0.97)
Ketoconazole | 200 mg b.i.d. | 400/100 mg b.i.d. | 15 | ↑ | 2.11 (1.81–2.44) | 3.12 (2.65–3.68) | 9.68 (6.44–14.55)
R-Methadone | 55–150 mg q.d. | 600/100 mg b.i.d. | 16 | ↓ | 0.76 (0.71–0.81) | 0.84 (0.78–0.91) | 0.85 (0.77–0.94)
Omeprazole | 40 mg single dose | 600/100 mg b.i.d. | 12 | ↓ | 0.66 (0.48–0.90) | 0.58 (0.50–0.66) | -
5-hydroxy omeprazole |  |  |  | ↓ | 0.93 (0.71–1.21) | 0.84 (0.77–0.92) | -
Paroxetine | 20 mg q.d. | 400/100 mg b.i.d. | 16 | ↓ | 0.64 (0.59–0.71) | 0.61 (0.56–0.66) | 0.63 (0.55–0.73)
Pravastatin | 40 mg single dose | 600/100 mg b.i.d. | 14 | ↑ | 1.63 (0.95–2.82) | 1.81 (1.23–2.66) | -
Rifabutin | 150 mg q.o.d. [q.o.d. = every other day] when administered with PREZISTA/ritonavir | 600/100 mg b.i.d. [In comparison to rifabutin 300 mg q.d.] | 11 | ↑ | 0.72 (0.55–0.93) | 0.93 (0.80–1.09) | 1.64 (1.48–1.81)
25-O-desacetyl-rifabutin | 300 mg q.d. when administered alone |  | 11 | ↑ | 4.77 (4.04–5.63) | 9.81 (8.09–11.9) | 27.1 (22.2–33.2)
Sertraline | 50 mg q.d. | 400/100 mg b.i.d. | 13 | ↓ | 0.56 (0.49–0.63) | 0.51 (0.46–0.58) | 0.51 (0.45–0.57)
Sildenafil | 100 mg (single dose) administered alone | 400/100 mg b.i.d. | 16 | ↑ | 0.62 (0.55–0.70) | 0.97 (0.86–1.09) | -
 | 25 mg (single dose) when administered with darunavir/ritonavir
S-warfarin | 10 mg single dose | 600/100 mg b.i.d. | 12 | ↓ | 0.92 (0.86–0.97) | 0.79 (0.73–0.85) | -
7-OH-S-warfarin |  |  | 12 | ↑ | 1.42 (1.24–1.63) | 1.23 (0.97–1.57) | -
N = number of subjects with data;- = no information available
A cocktail study was conducted in 12 healthy volunteers to evaluate the effect of steady state pharmacokinetics of darunavir/ritonavir on the activity of CYP2D6 (using dextromethorphan as probe substrate), CYP2C9 (using warfarin as probe substrate), and CYP2C19 (using omeprazole as probe substrate). The pharmacokinetic results are shown in Table 13.

12.4 Microbiology

Mechanism of Action

Darunavir is an inhibitor of the HIV-1 protease. It selectively inhibits the cleavage of HIV-1 encoded Gag-Pol polyproteins in infected cells, thereby preventing the formation of mature virus particles.

Antiviral Activity

Darunavir exhibits activity against laboratory strains and clinical isolates of HIV-1 and laboratory strains of HIV-2 in acutely infected T-cell lines, human peripheral blood mononuclear cells and human monocytes/macrophages with median EC50 values ranging from 1.2 to 8.5 nM (0.7 to 5.0 ng/mL). Darunavir demonstrates antiviral activity in cell culture against a broad panel of HIV-1 group M (A, B, C, D, E, F, G), and group O primary isolates with EC50 values ranging from less than 0.1 to 4.3 nM. The EC50 value of darunavir increases by a median factor of 5.4 in the presence of human serum. Darunavir did not show antagonism when studied in combination with the PIs amprenavir, atazanavir, indinavir, lopinavir, nelfinavir, ritonavir, saquinavir, or tipranavir, the N(t)RTIs abacavir, didanosine, emtricitabine, lamivudine, stavudine, tenofovir, zalcitabine, or zidovudine, the NNRTIs delavirdine, efavirenz, etravirine, or nevirapine, and the fusion inhibitor enfuvirtide.

Resistance

Cell Culture: HIV-1 isolates with a decreased susceptibility to darunavir have been selected in cell culture and obtained from subjects treated with darunavir/ritonavir. Darunavir-resistant virus derived in cell culture from wild-type HIV-1 had 21- to 88-fold decreased susceptibility to darunavir and developed 2 to 4 of the following amino acid substitutions S37D, R41E/T, K55Q, H69Q, K70E, T74S, V77I, or I85V in the protease. Selection in cell culture of darunavir resistant HIV-1 from nine HIV-1 strains harboring multiple PI resistance-associated mutations resulted in the overall emergence of 22 mutations in the protease gene, coding for amino acid substitutions L10F, V11I, I13V, I15V, G16E, L23I, V32I, L33F, S37N, M46I, I47V, I50V, F53L, L63P, A71V, G73S, L76V, V82I, I84V, T91A/S, and Q92R, of which L10F, V32I, L33F, S37N, M46I, I47V, I50V, L63P, A71V, and I84V were the most prevalent. These darunavir-resistant viruses had at least eight protease substitutions and exhibited 50- to 641-fold decreases in darunavir susceptibility with final EC50 values ranging from 125 nM to 3461 nM.

Clinical studies of PREZISTA/ritonavir in treatment-experienced subjects: In a pooled analysis of the 600/100 mg PREZISTA/ritonavir twice daily arms of Studies TMC114-C213, TMC114-C202, TMC114-C215, and the control arms of etravirine studies TMC125-C206 and TMC125-C216, the amino acid substitutions V32I and I54L or M developed most frequently on PREZISTA/ritonavir in 41% and 25%, respectively, of the treatment-experienced subjects who experienced virologic failure, either by rebound or by never being suppressed (less than 50 copies/mL). Other substitutions that developed frequently in PREZISTA/ritonavir virologic failure isolates occurred at amino acid positions V11I, I15V, L33F, I47V, I50V, and L89V. These amino acid substitutions were associated with decreased susceptibility to darunavir; 90% of the virologic failure isolates had a greater than 7-fold decrease in susceptibility to darunavir at failure. The median darunavir phenotype (fold change from reference) of the virologic failure isolates was 4.3-fold at baseline and 85-fold at failure. Amino acid substitutions were also observed in the protease cleavage sites in the Gag polyprotein of some PREZISTA/ritonavir virologic failure isolates. In Study TMC114-C212 of treatment-experienced pediatric subjects, the amino acid substitutions V32I, I54L and L89M developed most frequently in virologic failures on PREZISTA/ritonavir.

In the 96-week as-treated analysis of the Phase 3 Study TMC114-C214, the percent of virologic failures (never suppressed, rebounders and discontinued before achieving suppression) was 21% (62/298) in the group of subjects receiving PREZISTA/ritonavir 600/100 mg twice daily compared to 32% (96/297) of subjects receiving lopinavir/ritonavir 400/100 mg twice daily. Examination of subjects who failed on PREZISTA/ritonavir 600/100 mg twice daily and had post-baseline genotypes and phenotypes showed that 7 subjects (7/43; 16%) developed PI substitutions on darunavir/ritonavir treatment resulting in decreased susceptibility to darunavir. Six of the 7 had baseline PI resistance-associated substitutions and baseline darunavir phenotypes greater than 7. The most common emerging PI substitutions in these virologic failures were V32I, L33F, M46I or L, I47V, I54L, T74P and L76V. These amino acid substitutions were associated with 59- to 839-fold decreased susceptibility to darunavir at failure. Examination of individual subjects who failed in the comparator arm on lopinavir/ritonavir and had post-baseline genotypes and phenotypes showed that 31 subjects (31/75; 41%) developed substitutions on lopinavir treatment resulting in decreased susceptibility to lopinavir (greater than 10-fold) and the most common substitutions emerging on treatment were L10I or F, M46I or L, I47V or A, I54V and L76V. Of the 31 lopinavir/ritonavir virologic failure subjects, 14 had reduced susceptibility (greater than 10-fold) to lopinavir at baseline.

In the 48-week analysis of the Phase 3 Study TMC114-C229, the number of virologic failures (including those who discontinued before suppression after Week 4) was 26% (75/294) in the group of subjects receiving PREZISTA/ritonavir 800/100 mg once daily compared to 19% (56/296) of subjects receiving PREZISTA/ritonavir 600/100 mg twice daily. Examination of isolates from subjects who failed on PREZISTA/ritonavir 800/100 mg once daily and had post-baseline genotypes showed that 8 subjects (8/60; 13%) had isolates that developed IAS-USA defined PI resistance-associated substitutions compared to 5 subjects (5/39; 13%) on PREZISTA/ritonavir 600/100 mg twice daily. Isolates from 2 subjects developed PI resistance associated substitutions associated with decreased susceptibility to darunavir; 1 subject isolate in the PREZISTA/ritonavir 800/100 mg once daily arm, developed substitutions V32I, M46I, L76V and I84V associated with a 24-fold decreased susceptibility to darunavir, and 1 subject isolate in the PREZISTA/ritonavir 600/100 mg twice daily arm developed substitutions L33F and I50V associated with a 40-fold decreased susceptibility to darunavir. In the PREZISTA/ritonavir 800/100 mg once daily and PREZISTA/ritonavir 600/100 mg twice daily groups, isolates from 7 (7/60, 12%) and 4 (4/42, 10%) virologic failures, respectively, developed decreased susceptibility to an NRTI included in the treatment regimen.

Clinical studies of PREZISTA/ritonavir in treatment-naive subjects: In the 192-week as-treated analysis censoring those who discontinued before Week 4 of the Phase 3 Study TMC114-C211, the percentage of virologic failures (never suppressed, rebounders and discontinued before achieving suppression) was 22% (64/288) in the group of subjects receiving PREZISTA/ritonavir 800/100 mg once daily compared to 29% (76/263) of subjects receiving lopinavir/ritonavir 800/200 mg per day. In the PREZISTA/ritonavir arm, emergent PI resistance-associated substitutions were identified in 11 of the virologic failures with post-baseline genotypic data (n=43). However, none of the darunavir virologic failures had a decrease in darunavir susceptibility (greater than 7-fold change) at failure. In the comparator lopinavir/ritonavir arm, emergent PI resistance-associated substitutions were identified in 17 of the virologic failures with post-baseline genotypic data (n=53), but none of the lopinavir/ritonavir virologic failures had decreased susceptibility to lopinavir (greater than 10-fold change) at failure. The reverse transcriptase M184V substitution and/or resistance to emtricitabine, which was included in the fixed background regimen, was identified in 4 virologic failures from the PREZISTA/ritonavir arm and 7 virologic failures in the lopinavir/ritonavir arm.

Cross-resistance

Cross-resistance among PIs has been observed. Darunavir has a less than 10-fold decreased susceptibility in cell culture against 90% of 3309 clinical isolates resistant to amprenavir, atazanavir, indinavir, lopinavir, nelfinavir, ritonavir, saquinavir and/or tipranavir showing that viruses resistant to these PIs remain susceptible to darunavir.

Darunavir-resistant viruses were not susceptible to amprenavir, atazanavir, indinavir, lopinavir, nelfinavir, ritonavir or saquinavir in cell culture. However, six of nine darunavir-resistant viruses selected in cell culture from PI-resistant viruses showed a fold change in EC50 values less than 3 for tipranavir, indicative of limited cross-resistance between darunavir and tipranavir. In Studies TMC114-C213, TMC114-C202, and TMC114-C215, 34% (64/187) of subjects in the darunavir/ritonavir arm whose baseline isolates had decreased susceptibility to tipranavir (tipranavir fold change greater than 3) achieved less than 50 copies/mL serum HIV-1 RNA levels at Week 96. Of the viruses isolated from subjects experiencing virologic failure on PREZISTA/ritonavir 600/100 mg twice daily (greater than 7 fold change), 41% were still susceptible to tipranavir and 10% were susceptible to saquinavir while less than 2% were susceptible to the other protease inhibitors (amprenavir, atazanavir, indinavir, lopinavir or nelfinavir).

In Study TMC114-C214, the 7 darunavir/ritonavir virologic failures with reduced susceptibility to darunavir at failure were also resistant to the approved PIs (fos)amprenavir, atazanavir, lopinavir, indinavir, and nelfinavir at failure. Six of these 7 were resistant to saquinavir and 5 were resistant to tipranavir. Four of these virologic failures were already PI-resistant at baseline.

Cross-resistance between darunavir and nucleoside/nucleotide reverse transcriptase inhibitors, non-nucleoside reverse transcriptase inhibitors, fusion inhibitors, CCR5 co-receptor antagonists, or integrase inhibitors is unlikely because the viral targets are different.

Baseline Genotype/Phenotype and Virologic Outcome Analyses

Genotypic and/or phenotypic analysis of baseline virus may aid in determining darunavir susceptibility before initiation of PREZISTA/ritonavir 600/100 mg twice daily therapy. The effect of baseline genotype and phenotype on virologic response at 96 weeks was analyzed in as-treated analyses using pooled data from the Phase 2b studies (Studies TMC114-C213, TMC114-C202, and TMC114-C215) (n=439). The findings were confirmed with additional genotypic and phenotypic data from the control arms of etravirine Studies TMC125-C206 and TMC125-C216 at Week 24 (n=591).

Diminished virologic responses were observed in subjects with 5 or more baseline IAS-defined primary protease inhibitor resistance-associated substitutions (D30N, V32I, L33F, M46I/L, I47A/V, G48V, I50L/V, I54L/M, L76V, V82A/F/L/S/T, I84V, N88S, L90M) (see Table 14).

Table 14: Response to PREZISTA/ritonavir 600/100 mg Twice Daily by Baseline Number of IAS-Defined Primary PI Resistance-Associated Substitutions: As-treated Analysis of Studies TMC114-C213, TMC114-C202, and TMC114-C215
 | Studies TMC114-C213, TMC114-C202, TMC114-C215 < 50 copies/mL at Week 96 N=439
# IAS-Defined Primary PI Substitutions | Overall | De Novo ENF | Re-Used/ No ENF
All | 44% (192/439) | 54% (61/112) | 40% (131/327)
0 – 4 | 50% (162/322) | 58% (49/85) | 48% (113/237)
5 | 22% (16/74) | 47% (9/19) | 13% (7/55)
≥ 6 | 9% (3/32) | 17% (1/6) | 8% (2/26)
IAS Primary PI Substitutions (2008): D30N, V32I, L33F, M46I/L, I47A/V, G48V, I50L/V, I54L/M, L76V, V82A/F/L/S/T, I84V, N88S, L90M

The presence at baseline of two or more of the substitutions V11I, V32I, L33F, I47V, I50V, I54L or M, T74P, L76V, I84V or L89V was associated with a decreased virologic response to PREZISTA/ritonavir. In subjects not taking enfuvirtide de novo, the proportion of subjects achieving viral load less than 50 plasma HIV-1 RNA copies/mL at 96 weeks was 59%, 29%, and 12% when the baseline genotype had 0–1, 2 and greater than or equal to 3 of these substitutions, respectively.

Baseline darunavir phenotype (shift in susceptibility relative to reference) was shown to be a predictive factor of virologic outcome. Response rates assessed by baseline darunavir phenotype are shown in Table 15. These baseline phenotype groups are based on the select patient populations in the Studies TMC114-C213, TMC114-C202, and TMC114-C215, and are not meant to represent definitive clinical susceptibility breakpoints for PREZISTA/ritonavir. The data are provided to give clinicians information on the likelihood of virologic success based on pre-treatment susceptibility to darunavir.

Table 15: Response (HIV-1 RNA < 50 copies/mL at Week 96) to PREZISTA/ritonavir 600/100 mg Twice Daily by Baseline Darunavir Phenotype and by Use of Enfuvirtide (ENF): As-treated Analysis of Studies TMC114-C213, TMC114-C202, and TMC114-C215
 | Proportion of Subjects with < 50 copies/mL at Week 96 N=417
Baseline DRV Phenotype | All | De Novo ENF | Re-Used/ No ENF
Overall | 175/417 (42%) | 61/112 (54%) | 131/327 (40%)
0 – 7 | 148/270 (55%) | 44/65 (68%) | 104/205 (51%)
> 7 – 20 | 16/53 (30%) | 7/17 (41%) | 9/36 (25%)
> 20 | 11/94 (12%) | 6/23 (26%) | 5/71 (7%)

13 NONCLINICAL TOXICOLOGY

13.1 Carcinogenesis, Mutagenesis, Impairment of Fertility

Carcinogenesis and Mutagenesis

Darunavir was evaluated for carcinogenic potential by oral gavage administration to mice and rats up to 104 weeks. Daily doses of 150, 450 and 1000 mg/kg were administered to mice and doses of 50, 150 and 500 mg/kg was administered to rats. A dose-related increase in the incidence of hepatocellular adenomas and carcinomas were observed in males and females of both species as well as an increase in thyroid follicular cell adenomas in male rats. The observed hepatocellular findings in rodents are considered to be of limited relevance to humans. Repeated administration of darunavir to rats caused hepatic microsomal enzyme induction and increased thyroid hormone elimination, which predispose rats, but not humans, to thyroid neoplasms. At the highest tested doses, the systemic exposures to darunavir (based on AUC) were between 0.4- and 0.7-fold (mice) and 0.7- and 1-fold (rats), relative to those observed in humans at the recommended therapeutic doses (600/100 mg twice daily or 800/100 mg once daily).

Darunavir was not mutagenic or genotoxic in a battery of in vitro and in vivo assays including bacterial reserve mutation (Ames), chromosomal aberration in human lymphocytes and in vivo micronucleus test in mice.

Impairment of Fertility

No effects on fertility or early embryonic development were observed with darunavir in rats and darunavir has shown no teratogenic potential in mice or rats (in the presence or absence of ritonavir), and rabbits.

13.2 Animal Toxicology and/or Pharmacology

In juvenile rats single doses of darunavir (20 mg/kg to 160 mg/kg at ages 5–11 days) or multiple doses of darunavir (40 mg/kg to 1000 mg/kg at age 12 days) caused mortality. The mortalities were associated with convulsions in some of the animals. Within this age range exposures in plasma, liver and brain were dose and age dependent and were considerably greater than those observed in adult rats. These findings were attributed to the ontogeny of the CYP450 liver enzymes involved in the metabolism of darunavir and the immaturity of the blood-brain barrier. No treatment-related mortalities were noted in juvenile rats after a single dose of darunavir at 1000 mg/kg on day 26 of age or after repeat dosing at 500 mg/kg from day 23 to 50 of age. The exposures and toxicity profile in the older animals (day 23 or day 26) were comparable to those observed in adult rats. Due to uncertainties regarding the rate of development of the human blood-brain barrier and liver enzymes, do not administer PREZISTA/ritonavir in pediatric patients below 3 years of age.

14 CLINICAL STUDIES

14.1 Description of Adult Clinical Studies

The evidence of efficacy of PREZISTA/ritonavir is based on the analyses of 192-week data from a randomized, controlled open-label Phase 3 trial in treatment-naïve (TMC114-C211) HIV-1-infected adult subjects and 96-week data from a randomized, controlled, open-label Phase 3 trial in antiretroviral treatment-experienced (TMC114-C214) HIV-1-infected adult subjects. In addition, 96-week data are included from 2 randomized, controlled Phase 2b trials, TMC114-C213 and TMC114-C202, in antiretroviral treatment-experienced HIV-1-infected adult subjects.

14.2 Treatment-Naïve Adult Subjects

Study TMC114-C211

Study TMC114-C211 is a randomized, controlled, open-label Phase 3 trial comparing PREZISTA/ritonavir 800/100 mg once daily versus lopinavir/ritonavir 800/200 mg per day (given as a twice daily or as a once daily regimen) in antiretroviral treatment-naïve HIV-1-infected adult subjects. Both arms used a fixed background regimen consisting of tenofovir disoproxil fumarate 300 mg once daily (TDF) and emtricitabine 200 mg once daily (FTC).

HIV-1-infected subjects who were eligible for this trial had plasma HIV-1 RNA greater than or equal to 5000 copies/mL. Randomization was stratified by screening plasma viral load (HIV-1 RNA less than 100,000 copies/mL or greater than or equal to 100,000 copies/mL) and screening CD4+ cell count (less than 200 cells/mm^3 or greater than or equal to 200 cells/mm^3). Virologic response was defined as a confirmed plasma HIV-1 RNA viral load less than 50 copies/mL. Analyses included 689 subjects in Study TMC114-C211 who had completed 192 weeks of treatment or discontinued earlier.

Demographics and baseline characteristics were balanced between the PREZISTA/ritonavir arm and the lopinavir/ritonavir arm (see Table 16). Table 16 compares the demographic and baseline characteristics between subjects in the PREZISTA/ritonavir 800/100 mg once daily arm and subjects in the lopinavir/ritonavir 800/200 mg per day arm in Study TMC114-C211.

Table 16: Demographic and Baseline Characteristics of Subjects in Study TMC114-C211
 | Randomized Study TMC114-C211
 | PREZISTA/ritonavir 800/100 mg once daily + TDF/FTC N = 343 | lopinavir/ritonavir 800/200 mg per day + TDF/FTC N = 346
Demographic Characteristics
Median Age (years) (range, years) | 34 (18–70) | 33 (19–68)
Sex
Male | 70% | 70%
Female | 30% | 30%
Race
White | 40% | 45%
Black | 23% | 21%
Hispanic | 23% | 22%
Asian | 13% | 11%
Baseline Characteristics
Mean Baseline Plasma HIV-1 RNA (log10 copies/mL) | 4.86 | 4.84
Median Baseline CD4+ Cell Count (cells/mm^3) (range, cells/mm^3) | 228 (4–750) | 218 (2–714)
Percentage of Patients with Baseline Viral Load ≥ 100,000 copies/mL | 34% | 35%
Percentage of Patients with Baseline CD4+ Cell Count < 200 cells/mm^3 | 41% | 43%

Week 192 outcomes for subjects on PREZISTA/ritonavir 800/100 mg once daily from Study TMC114-C211 are shown in Table 17.

Table 17: Virologic Outcome of Randomized Treatment of Study TMC114-C211 at 192 Weeks
 | PREZISTA/ritonavir 800/100 mg once daily + TDF/FTC N = 343 | lopinavir/ritonavir 800/200 mg per day + TDF/FTC N = 346
Virologic success HIV-1 RNA < 50 copies/mL | 70% [95% CI: 1.9; 16.1] | 61%
Virologic failure [Includes patients who discontinued prior to Week 192 for lack or loss of efficacy and patients who are ≥ 50 copies in the 192-week window and patients who had a change in their background regimen that was not permitted by the protocol] | 12% | 15%
No virologic data at Week 192 window [Window 186–198 Weeks] Reasons
Discontinued study due to adverse event or death [Includes patients who discontinued due to adverse event or death at any time point from Day 1 through the time window if this resulted in no virologic data on treatment during the specified window] | 5% | 13%
Discontinued study for other reasons [Other includes: withdrew consent, loss to follow-up, etc., if the viral load at the time of discontinuation was < 50 copies/mL] | 13% | 12%
Missing data during window but on study | <1% | 0%
N = total number of subjects with data

In Study TMC114-C211 at 192 weeks of treatment, the median increase from baseline in CD4+ cell counts was 258 cells/mm^3 in the PREZISTA/ritonavir 800/100 mg once daily arm and 263 cells/mm^3 in the lopinavir/ritonavir 800/200 mg per day arm. Of the PREZISTA/ritonavir subjects with a confirmed virologic response of < 50 copies/mL at Week 48, 81% remained undetectable at Week 192 versus 68% with lopinavir/ritonavir. In the 192 week analysis, statistical superiority of the PREZISTA/ritonavir regimen over the lopinavir/ritonavir regimen was demonstrated for both ITT and OP populations.

14.3 Treatment-Experienced Adult Subjects

Study TMC114-C229

Study TMC114-C229 is a randomized, open-label trial comparing PREZISTA/ritonavir 800/100 mg once daily to PREZISTA/ritonavir 600/100 mg twice daily in treatment-experienced HIV-1-infected patients with screening genotype resistance test showing no darunavir resistance associated substitutions (i.e. V11I, V32I, L33F, I47V, I50V, I54L, I54M, T74P, L76V, I84V, L89V) and a screening viral load of greater than 1,000 HIV-1 RNA copies/mL. Both arms used an optimized background regimen consisting of greater than or equal to 2 NRTIs selected by the investigator.

HIV-1-infected subjects who were eligible for this trial were on a highly active antiretroviral therapy regimen (HAART) for at least 12 weeks. Virologic response was defined as a confirmed plasma HIV-1 RNA viral load less than 50 copies/mL. Analyses included 590 subjects who had completed 48 weeks of treatment or discontinued earlier.

Table 18 compares the demographic and baseline characteristics between subjects in the PREZISTA/ritonavir 800/100 mg once daily arm and subjects in the PREZISTA/ritonavir 600/100 mg twice daily arm in Study TMC114-C229. No imbalances between the 2 arms were noted.

Table 18: Demographic and Baseline Characteristics of Subjects in Study TMC114-C229
 | Randomized Study TMC114-C229
 | PREZISTA/ritonavir 800/100 mg once daily + OBR N = 294 | PREZISTA/ritonavir 600/100 mg twice daily + OBR N = 296
Demographic Characteristics
Median Age (years) (range, years) | 40 (18–70) | 40 (18–77)
Sex
Male | 61% | 67%
Female | 39% | 33%
Race
White | 35% | 37%
Black | 28% | 24%
Hispanic | 16% | 20%
Asian | 16% | 14%
Baseline Characteristics
Mean Baseline Plasma HIV-1 RNA (log10 copies/mL) | 4.19 | 4.13
Median Baseline CD4+ Cell Count (cells/mm^3) (range, cells/mm^3) | 219 (24–1306) | 236 (44–864)
Percentage of Patients with Baseline Viral Load ≥ 100,000 copies/mL | 13% | 11%
Percentage of Patients with Baseline CD4+ Cell Count < 200 cells/mm^3 | 43% | 39%
Median Darunavir Fold Change (range) [Based on phenotype (Antivirogram®)] | 0.50 (0.1–1.8) | 0.50 (0.1–1.9)
Median Number of Resistance-Associated [Johnson VA, Brun-Vézinet F, Clotet B, et al. Update of the drug resistance mutations in HIV-1: December 2008. Top HIV Med 2008; 16(5): 138–145] :
PI mutations | 3 | 4
NNRTI mutations | 2 | 1
NRTI mutations | 1 | 1
Percentage of Subjects Susceptible to All Available PIs at Baseline | 88% | 86%
Percentage of Subjects with Number of Baseline Primary Protease Inhibitor Mutations :
0 | 84% | 84%
1 | 8% | 9%
2 | 5% | 4%
≥ 3 | 3% | 2%
Median Number of ARVs Previously Used [Only counting ARVs, excluding low-dose ritonavir] :
NRTIs | 3 | 3
NNRTIs | 1 | 1
PIs (excluding low-dose ritonavir) | 1 | 1

Week 48 outcomes for subjects on PREZISTA/ritonavir 800/100 mg once daily from Study TMC114-C229 are shown in Table 19.

Table 19: Virologic Outcome of Randomized Treatment of Study TMC114-C229 at 48 Weeks
 | Randomized Study TMC114-C229
 | PREZISTA/ritonavir 800/100 mg once daily + OBR N = 294 | PREZISTA/ritonavir 600/100 mg twice daily + OBR N = 296
Virologic success HIV-1 RNA < 50 copies/mL | 69% | 69%
Virologic failure [Includes patients who discontinued prior to Week 48 for lack or loss of efficacy, patients who are ≥ 50 copies in the 48-week window, patients who had a change in their background regimen that was not permitted in the protocol (provided the switch occurred before the earliest onset of an AE leading to permanent stop of study medication) and patients who discontinued for reasons other than AEs/death and lack or loss of efficacy (provided their last available viral load was detectable (HIV RNA ≥ 50 copies/mL).] | 26% | 23%
No virologic data at Week 48 window [Window 42–54 Weeks] Reasons
Discontinued study due to adverse event or death [Patients who discontinued due to adverse event or death at any time point from Day 1 through the time window if this resulted in no virologic data on treatment during the specified window.] | 3% | 4%
Discontinued study for other reasons [Other includes: withdrew consent, loss to follow-up, etc., if the viral load at the time of discontinuation was < 50 copies/mL.] | 2% | 3%
Missing data during window but on study | 0% | < 1%
N = total number of subjects with data

The mean increase from baseline in CD4+ cell counts was comparable for both treatment arms (108 cells/mm^3 and 112 cells/mm^3 in the PREZISTA/ritonavir 800/100 mg once daily arm and the PREZISTA/ritonavir 600/100 mg twice daily arm, respectively).

Study TMC114-C214

Study TMC114-C214 is a randomized, controlled, open-label Phase 3 trial comparing PREZISTA/ritonavir 600/100 mg twice daily versus lopinavir/ritonavir 400/100 mg twice daily in antiretroviral treatment-experienced, lopinavir/ritonavir-naïve HIV-1-infected adult subjects. Both arms used an optimized background regimen (OBR) consisting of at least 2 antiretrovirals (NRTIs with or without NNRTIs).

HIV-1-infected subjects who were eligible for this trial had plasma HIV-1 RNA greater than 1000 copies/mL and were on a highly active antiretroviral therapy regimen (HAART) for at least 12 weeks. Virologic response was defined as a confirmed plasma HIV-1 RNA viral load less than 400 copies/mL. Analyses included 595 subjects in Study TMC114-C214 who had completed 96 weeks of treatment or discontinued earlier.

Demographics and baseline characteristics were balanced between the PREZISTA/ritonavir arm and the lopinavir/ritonavir arm (see Table 20). Table 20 compares the demographic and baseline characteristics between subjects in the PREZISTA/ritonavir 600/100 mg twice daily arm and subjects in the lopinavir/ritonavir 400/100 mg twice daily arm in Study TMC114-C214.

Table 20: Demographic and Baseline Characteristics of Subjects in Study TMC114-C214
 | Randomized Study TMC114-C214
 | PREZISTA/ritonavir 600/100 mg twice daily + OBR N = 298 | lopinavir/ritonavir 400/100 mg twice daily + OBR N = 297
Demographic Characteristics
Median Age (years) (range, years) | 40 (18–68) | 41 (22–76)
Sex
Male | 77% | 81%
Female | 23% | 19%
Race
White | 54% | 57%
Black | 18% | 17%
Hispanic | 15% | 15%
Asian | 9% | 9%
Baseline Characteristics
Mean Baseline Plasma HIV-1 RNA (log10 copies/mL) | 4.33 | 4.28
Median Baseline CD4+ Cell Count (cells/mm^3) (range, cells/mm^3) | 235 (3–831) | 230 (2–1096)
Percentage of Patients with Baseline Viral Load ≥ 100,000 copies/mL | 19% | 17%
Percentage of Patients with Baseline CD4+ Cell Count < 200 cells/mm^3 | 40% | 40%
Median Darunavir Fold Change (range) | 0.60 (0.10–37.40) | 0.60 (0.1–43.8)
Median Lopinavir Fold Change (range) | 0.70 (0.40–74.40) | 0.80 (0.30–74.50)
Median Number of Resistance-Associated [Johnson VA, Brun-Vezinet F, Clotet B, et al. Update of the drug resistance mutations in HIV-1: Fall 2006. Top HIV Med 2006; 14(3): 125–130] :
PI mutations | 4 | 4
NNRTI mutations | 1 | 1
NRTI mutations | 2 | 2
Percentage of Subjects with Number of Baseline Primary Protease Inhibitor Mutations:
≤ 1 | 78% | 80%
2 | 8% | 9%
≥ 3 | 13% | 11%
Median Number of ARVs Previously Used [Only counting ARVs, excluding low-dose ritonavir] :
NRTIs | 4 | 4
NNRTIs | 1 | 1
PIs (excluding low-dose ritonavir) | 1 | 1
Percentage of Subjects Resistant [Based on phenotype (Antivirogram®)] to All Available [Commercially available PIs at the time of study enrollment] PIs at Baseline, excluding Darunavir | 2% | 3%

Week 96 outcomes for subjects on PREZISTA/ritonavir 600/100 mg twice daily from Study TMC114-C214 are shown in Table 21.

Table 21: Virologic Outcome of Randomized Treatment of Study TMC114-C214 at 96 Weeks
 | PREZISTA/ritonavir 600/100 mg twice daily + OBR N = 298 | lopinavir/ritonavir 400/100 mg twice daily + OBR N = 297
Virologic success HIV-1 RNA < 50 copies/mL | 58% | 52%
Virologic failure [Includes patients who discontinued prior to Week 96 for lack or loss of efficacy and patients who are ≥ 50 copies in the 96-week window and patients who had a change in their OBR that was not permitted by the protocol.] | 26% | 33%
No virologic data at Week 96 window [Window 90–102 Weeks] Reasons
Discontinued study due to adverse event or death [Includes patients who discontinued due to adverse event or death at any time point from Day 1 through the time window if this resulted in no virologic data on treatment during the specified window.] | 7% | 8%
Discontinued study for other reasons [Other includes: withdrew consent, loss to follow-up, etc., if the viral load at the time of discontinuation was < 50 copies/mL.] | 8% | 7%
Missing data during window but on study | 1% | < 1%
N = total number of subjects with data

In Study TMC114-C214 at 96 weeks of treatment, the median increase from baseline in CD4+ cell counts was 81 cells/mm^3 in the PREZISTA/ritonavir 600/100 mg twice daily arm and 93 cells/mm^3 in the lopinavir/ritonavir 400/100 mg twice daily arm.

Studies TMC114-C213 and TMC114-C202

Studies TMC114-C213 and TMC114-C202 are randomized, controlled, Phase 2b trials in adult subjects with a high level of PI resistance consisting of 2 parts: an initial partially-blinded, dose-finding part and a second long-term part in which all subjects randomized to PREZISTA/ritonavir received the recommended dose of 600/100 mg twice daily.

HIV-1-infected subjects who were eligible for these trials had plasma HIV-1 RNA greater than 1000 copies/mL, had prior treatment with PI(s), NNRTI(s) and NRTI(s), had at least one primary PI mutation (D30N, M46I/L, G48V, I50L/V, V82A/F/S/T, I84V, L90M) at screening, and were on a stable PI-containing regimen at screening for at least 8 weeks. Randomization was stratified by the number of PI mutations, screening viral load, and the use of enfuvirtide.

The virologic response rate was evaluated in subjects receiving PREZISTA/ritonavir plus an OBR versus a control group receiving an investigator-selected PI(s) regimen plus an OBR. Prior to randomization, PI(s) and OBR were selected by the investigator based on genotypic resistance testing and prior ARV history. The OBR consisted of at least 2 NRTIs with or without enfuvirtide. Selected PI(s) in the control arm included: lopinavir in 36%, (fos)amprenavir in 34%, saquinavir in 35% and atazanavir in 17%; 98% of control subjects received a ritonavir boosted PI regimen out of which 23% of control subjects used dual-boosted PIs. Approximately 47% of all subjects used enfuvirtide, and 35% of the use was in subjects who were ENF-naïve. Virologic response was defined as a decrease in plasma HIV-1 RNA viral load of at least 1 log10 versus baseline.

In the pooled analysis for TMC114-C213 and TMC114-C202, demographics and baseline characteristics were balanced between the PREZISTA/ritonavir arm and the comparator PI arm (see Table 22). Table 22 compares the demographic and baseline characteristics between subjects in the PREZISTA/ritonavir 600/100 mg twice daily arm and subjects in the comparator PI arm in the pooled analysis of Studies TMC114-C213 and TMC114-C202.

Table 22: Demographic and Baseline Characteristics of Subjects in the Studies TMC114-C213 and TMC114-C202 (Pooled Analysis)
 | Randomized Studies TMC114-C213 and TMC114-C202
 | PREZISTA/ritonavir 600/100 mg twice daily + OBR N = 131 | Comparator PI(s) + OBR N = 124
Demographic Characteristics
Median Age (years) (range, years) | 43 (27–73) | 44 (25–65)
Sex
Male | 89% | 88%
Female | 11% | 12%
Race
White | 81% | 73%
Black | 10% | 15%
Hispanic | 7% | 8%
Baseline Characteristics
Mean Baseline Plasma HIV-1 RNA (log10 copies/mL) | 4.61 | 4.49
Median Baseline CD4+ Cell Count (cells/mm^3) (range, cells/mm^3) | 153 (3–776) | 163 (3–1274)
Percentage of Patients with Baseline Viral Load > 100,000 copies/mL | 24% | 29%
Percentage of Patients with Baseline CD4+ Cell Count < 200 cells/mm^3 | 67% | 58%
Median Darunavir Fold Change | 4.3 | 3.3
Median Number of Resistance-Associated [Johnson VA, Brun-Vezinet F, Clotet B, et al. Update of the drug resistance mutations in HIV-1: Fall 2006. Top HIV Med 2006; 14(3): 125–130] :
PI mutations | 12 | 12
NNRTI mutations | 1 | 1
NRTI mutations | 5 | 5
Percentage of Subjects with Number of Baseline Primary Protease Inhibitor Mutations:
≤ 1 | 8% | 9%
2 | 22% | 21%
≥ 3 | 70% | 70%
Median Number of ARVs Previously Used [Based on phenotype (Antivirogram®)] :
NRTIs | 6 | 6
NNRTIs | 1 | 1
PIs (excluding low-dose ritonavir) | 5 | 5
Percentage of Subjects Resistant to All Available [Commercially available PIs at the time of study enrollment] PIs at Baseline, excluding Tipranavir and Darunavir | 63% | 61%
Percentage of Subjects with Prior Use of Enfuvirtide | 20% | 17%

Week 96 outcomes for subjects on the recommended dose PREZISTA/ritonavir 600/100 mg twice daily from the pooled Studies TMC114-C213 and TMC114-C202 are shown in Table 23.

Table 23: Outcomes of Randomized Treatment Through Week 96 of the Studies TMC114-C213 and TMC114-C202 (Pooled Analysis)
 | Randomized Studies TMC114-C213 and TMC114-C202
 | PREZISTA/ritonavir 600/100 mg twice daily + OBR N=131 | Comparator PI(s) + OBR N=124
Virologic Responders confirmed at least 1 log10 HIV-1 RNA below baseline through Week 96 (< 50 copies/mL at Week 96) | 57% (39%) | 10% (9%)
Virologic failures | 29% | 80%
Lack of initial response [Subjects who did not achieve at least a confirmed 0.5 log10 HIV-1 RNA drop from baseline at Week 12] | 8% | 53%
Rebounder [Subjects with an initial response (confirmed 1 log10 drop in viral load), but without a confirmed 1 log10 drop in viral load at Week 96] | 17% | 19%
Never Suppressed [Subjects who never reached a confirmed 1 log10 drop in viral load before Week 96] | 4% | 8%
Death or discontinuation due to adverse events | 9% | 3%
Discontinuation due to other reasons | 5% | 7%

In the pooled Studies TMC114-C213 and TMC114-C202 through 48 weeks of treatment, the proportion of subjects with HIV-1 RNA less than 400 copies/mL in the arm receiving PREZISTA/ritonavir 600/100 mg twice daily compared to the comparator PI arm was 55.0% and 14.5%, respectively. In addition, the mean changes in plasma HIV-1 RNA from baseline were –1.69 log10 copies/mL in the arm receiving PREZISTA/ritonavir 600/100 mg twice daily and –0.37 log10 copies/mL for the comparator PI arm. The mean increase from baseline in CD4+ cell counts was higher in the arm receiving PREZISTA/ritonavir 600/100 mg twice daily (103 cells/mm^3) than in the comparator PI arm (17 cells/mm^3).

14.4 Pediatric Patients

The pharmacokinetic profile, safety and antiviral activity of PREZISTA/ritonavir were evaluated in 2 randomized, open-label, multicenter studies.

Study TMC114-C212

Treatment-experienced pediatric subjects between the ages of 6 and less than 18 years and weighing at least 20 kg were stratified according to their weight (greater than or equal to 20 kg to less than 30 kg, greater than or equal to 30 kg to less than 40 kg, greater than or equal to 40 kg) and received PREZISTA tablets with either ritonavir capsules or oral solution plus background therapy consisting of at least two non-protease inhibitor antiretroviral drugs. Eighty patients were randomized and received at least one dose of PREZISTA/ritonavir. Pediatric subjects who were at risk of discontinuing therapy due to intolerance of ritonavir oral solution (e.g., taste aversion) were allowed to switch to the capsule formulation. Of the 44 pediatric subjects taking ritonavir oral solution, 23 subjects switched to the 100 mg capsule formulation and exceeded the weight-based ritonavir dose without changes in observed safety.

The 80 randomized pediatric subjects had a median age of 14 (range 6 to less than 18 years), and were 71% male, 54% Caucasian, 30% Black, 9% Hispanic and 8% other. The mean baseline plasma HIV-1 RNA was 4.64 log10 copies/mL, and the median baseline CD4+ cell count was 330 cells/mm^3 (range: 6 to 1505 cells/mm^3). Overall, 38% of pediatric subjects had baseline plasma HIV-1 RNA ≥ 100,000 copies/mL. Most pediatric subjects (79%) had previous use of at least one NNRTI and 96% of pediatric subjects had previously used at least one PI.

Seventy-seven pediatric subjects (96%) completed the 24-week period. Of the patients who discontinued, one patient discontinued treatment due to an adverse event. An additional 2 patients discontinued for other reasons, one patient due to compliance and another patient due to relocation.

The proportion of pediatric subjects with HIV-1 RNA less than 400 copies/mL and less than 50 copies/mL was 64% and 50%, respectively. The mean CD4+ cell count increase from baseline was 117 cells/mm^3.

Study TMC114-C228

Treatment-experienced pediatric subjects between the ages of 3 and less than 6 years and weighing greater than or equal to 10 kg to less than 20 kg received PREZISTA oral suspension with ritonavir oral solution plus background therapy consisting of at least two active non-protease inhibitor antiretroviral drugs. Twenty-one subjects received at least one dose of PREZISTA/ritonavir.

The 21 subjects had a median age of 4.4 years (range 3 to less than 6 years), and were 48% male, 57% Black, 29%, Caucasian and 14% other. The mean baseline plasma HIV-1 was 4.34 log10 copies/mL, the median baseline CD4+ cell count was 927 × 10^6 cells/l (range: 209 to 2,429 × 10^6 cells/l) and the median baseline CD4+ percentage was 27.7% (range: 15.6% to 51.1%). Overall, 24% of subjects had a baseline plasma HIV-1 RNA greater than or equal to 100,000 copies/mL. All subjects had used greater than or equal to 2 NRTIs, 62% of subjects had used greater than or equal to 1 NNRTI and 76% had previously used at least one HIV PI.

Twenty subjects (95%) completed the 24 week period. One subject prematurely discontinued treatment due to vomiting assessed as related to ritonavir.

The proportion of subjects with HIV-1 RNA less than 50 copies/mL and less than 400 copies/mL was 57% and 81%, respectively. The mean change in CD4+ percentage from baseline was 4%. The mean change in CD4+ cell count from baseline was 109 × 10^6 cells/L.

Dose recommendations from the two studies were based on the following:

- Similar darunavir plasma exposures in children compared to adults, and
- Similar virologic response rates and safety profile in children compared to adults

16 HOW SUPPLIED/STORAGE AND HANDLING

PREZISTA (darunavir) 400 mg tablets are supplied as light orange, oval-shaped, film-coated tablets containing darunavir ethanolate equivalent to 400 mg of darunavir per tablet. Each tablet is debossed with "400MG" on one side and "TMC" on the other side.

PREZISTA (darunavir) 600 mg tablets are supplied as orange, oval-shaped, film-coated tablets containing darunavir ethanolate equivalent to 600 mg of darunavir per tablet. Each tablet is debossed with "600MG" on one side and "TMC" on the other side.

PREZISTA is packaged in bottles in the following configuration:

400 mg tablets—bottles of 60 (NDC 54868-5969-0)

600 mg tablets—bottles of 60 (NDC 54868-6369-0)

Storage:

PREZISTA Oral Suspension

- Store at 25°C (77°F); with excursions permitted to 15°–30°C (59°–86°F).
- Do not refrigerate or freeze. Avoid exposure to excessive heat.
- Store in the original container.
- Shake well before each usage.

PREZISTA Tablets

- Store at 25°C (77°F); with excursions permitted to 15°–30°C (59°–86°F).

17 PATIENT COUNSELING INFORMATION

[See FDA-Approved Patient Labeling (Patient Information)]

A statement to patients and healthcare providers is included on the product's bottle label: ALERT: Find out about medicines that should NOT be taken with PREZISTA. A Patient Package Insert for PREZISTA is available for patient information.

17.1 Information About Therapy with PREZISTA

PREZISTA is not a cure for HIV-1 infection and patients may continue to experience illnesses associated with HIV-1 infection, including opportunistic infections. Patients should remain under the care of a physician when using PREZISTA.

Patients should be advised to avoid doing things that can spread HIV-1 infection to others.

- Do not share needles or other injection equipment.
- Do not share personal items that can have blood or body fluids on them, like toothbrushes and razor blades.
- Do not have any kind of sex without protection. Always practice safe sex by using a latex or polyurethane condom to lower the chance of sexual contact with semen, vaginal secretions, or blood.
- Do not breastfeed. We do not know if PREZISTA can be passed to the baby through breast milk and whether it could harm the baby. Also, mothers with HIV-1 should not breastfeed because HIV-1 can be passed to the baby in the breast milk.

17.2 Instructions for Use

Patients should be advised to take PREZISTA and ritonavir (NORVIR®) with food every day as prescribed. Patients should be instructed to swallow whole tablets with a drink such as water or milk. PREZISTA must always be used with ritonavir (NORVIR®) in combination with other antiretroviral drugs. Patients should not alter the dose of either PREZISTA or ritonavir (NORVIR®), discontinue ritonavir (NORVIR®), or discontinue therapy with PREZISTA without consulting their physician.

Patients Taking PREZISTA Once Daily

If a patient misses a dose of PREZISTA or ritonavir (NORVIR®) by more than 12 hours, the patient should be told to wait and then take the next dose of PREZISTA and ritonavir (NORVIR®) at the regularly scheduled time. If the patient misses a dose of PREZISTA or ritonavir (NORVIR®) by less than 12 hours, the patient should be told to take PREZISTA and ritonavir (NORVIR®) immediately, and then take the next dose of PREZISTA and ritonavir (NORVIR®) at the regularly scheduled time. If a dose of PREZISTA or ritonavir (NORVIR®) is skipped, the patient should not double the next dose. Inform the patient that he or she should not take more or less than the prescribed dose of PREZISTA or ritonavir (NORVIR®).

Patients Taking PREZISTA Twice Daily

If a patient misses a dose of PREZISTA or ritonavir (NORVIR®) by more than 6 hours, the patient should be told to wait and then take the next dose of PREZISTA and ritonavir (NORVIR®) at the regularly scheduled time. If the patient misses a dose of PREZISTA or ritonavir (NORVIR®) by less than 6 hours, the patient should be told to take PREZISTA and ritonavir (NORVIR®) immediately, and then take the next dose of PREZISTA and ritonavir (NORVIR®) at the regularly scheduled time. If a dose of PREZISTA or ritonavir (NORVIR®) is skipped, the patient should not double the next dose. Inform the patient that he or she should not take more or less than the prescribed dose of PREZISTA or ritonavir (NORVIR®).

17.3 Hepatotoxicity

Patients should be informed that Drug-induced hepatitis (e.g., acute hepatitis, cytolytic hepatitis) has been reported with PREZISTA co-administered with 100 mg of ritonavir. Monitor liver function before and during therapy, especially in patients with underlying chronic hepatitis, cirrhosis, or in patients who have pre-treatment elevations of transaminases. Post-marketing cases of liver injury, including some fatalities, have been reported. Patients should be advised about the signs and symptoms of liver problems. These may include jaundice of the skin or eyes, dark (tea colored) urine, pale colored stools, nausea, vomiting, loss of appetite, or pain, aching or sensitivity in the right upper quadrant of the abdomen.

17.4 Severe Skin Reactions

Patients should be informed that skin reactions ranging from mild to severe, including Stevens-Johnson Syndrome and toxic epidermal necrolysis, have been reported with PREZISTA co-administered with 100 mg of ritonavir. Patients should be advised to discontinue PREZISTA/ritonavir immediately if signs or symptoms of severe skin reactions develop. These can include but are not limited to severe rash or rash accompanied with fever, general malaise, fatigue, muscle or joint aches, blisters, oral lesions, conjunctivitis, hepatitis and/or eosinophilia.

17.5 Drug Interactions

PREZISTA/ritonavir may interact with many drugs; therefore, patients should be advised to report to their healthcare provider the use of any other prescription or nonprescription medication or herbal products, including St. John's wort.

Patients receiving estrogen-based contraceptives should be instructed to use alternate contraceptive measures during therapy with PREZISTA/ritonavir because hormonal levels may decrease.

17.6 Fat Redistribution

Patients should be informed that redistribution or accumulation of body fat may occur in patients receiving antiretroviral therapy, including PREZISTA/ritonavir, and that the cause and long-term health effects of these conditions are not known at this time.

Manufactured by:
PREZISTA oral suspension
Janssen Pharmaceutica, N.V.
Beerse, Belgium

PREZISTA tablets
Janssen Ortho LLC, Gurabo, PR 00778

Manufactured for:
Janssen Therapeutics, Division of Janssen Products, LP, Titusville NJ 08560

NORVIR® is a registered trademark of its respective owner.

PREZISTA® is a registered trademark of Janssen Pharmaceuticals.

© Janssen Pharmaceuticals, Inc. 2006

Distributed by:
Physicians Total Care, Inc.
Tulsa, Oklahoma 74146

Patient Information

PREZISTA (pre-ZIS-ta)
(darunavir)
Oral Suspension

PREZISTA (pre-ZIS-ta)
(darunavir)
Tablets

Read this Patient Information before you start taking PREZISTA and each time you get a refill. There may be new information. This information does not take the place of talking to your healthcare provider about your medical condition or your treatment.

Also read the Patient Information leaflet for NORVIR® (ritonavir).

What is the most important information I should know about PREZISTA?

- PREZISTA can interact with other medicines and cause serious side effects. It is important to know the medicines that should not be taken with PREZISTA. See the section "Who should not take PREZISTA?"
- PREZISTA may cause liver problems. Some people taking PREZISTA in combination with NORVIR® (ritonavir) have developed liver problems which may be life-threatening. Your healthcare provider should do blood tests before and during your combination treatment with PREZISTA. If you have chronic hepatitis B or C infection, your healthcare provider should check your blood tests more often because you have an increased chance of developing liver problems.
- Tell your healthcare provider if you have any of the below signs and symptoms of liver problems.
  - Dark (tea colored) urine
  - yellowing of your skin or whites of your eyes
  - pale colored stools (bowel movements)
  - nausea
  - vomiting
  - pain or tenderness on your right side below your ribs
  - loss of appetite

PREZISTA may cause severe or life-threatening skin reactions or rash. Sometimes these skin reactions and skin rashes can become severe and require treatment in a hospital. You should call your healthcare provider immediately if you develop a rash. However, stop taking PREZISTA and ritonavir combination treatment and call your healthcare provider immediately if you develop any skin changes with symptoms below:

- fever
- tiredness
- muscle or joint pain
- blisters or skin lesions
- mouth sores or ulcers
- red or inflamed eyes, like "pink eye" (conjunctivitis)

Rash occurred more often in patients taking PREZISTA and raltegravir together than with either drug separately, but was generally mild.

See "What are the possible side effects of PREZISTA?" for more information about side effects.

What is PREZISTA?

PREZISTA is a prescription anti-HIV medicine used with ritonavir and other anti-HIV medicines to treat adults and children 3 years of age and older with human immunodeficiency virus (HIV-1) infection. PREZISTA is a type of anti-HIV medicine called a protease inhibitor. HIV is the virus that causes AIDS (Acquired Immune Deficiency Syndrome).

When used with other HIV medicines, PREZISTA may help to reduce the amount of HIV in your blood (called "viral load"). PREZISTA may also help to increase the number of white blood cells called CD4 (T) cell which help fight off other infections. Reducing the amount of HIV and increasing the CD4 (T) cell count may improve your immune system. This may reduce your risk of death or infections that can happen when your immune system is weak (opportunistic infections).

Children under 3 years of age should not take PREZISTA.

PREZISTA does not cure HIV infection or AIDS and you may continue to experience illnesses associated with HIV-1 infection, including opportunistic infections. You should remain under the care of a doctor when using PREZISTA.

Avoid doing things that can spread HIV-1 infection.

- Do not share needles or other injection equipment.
- Do not share personal items that can have blood or body fluids on them, like toothbrushes and razor blades.
- Do not have any kind of sex without protection. Always practice safe sex by using a latex or polyurethane condom to lower the chance of sexual contact with semen, vaginal secretions, or blood.

Ask your healthcare provider if you have any questions on how to prevent passing HIV to other people.

Who should not take PREZISTA?

Do not take PREZISTA with any of the following medicines:

- alfuzosin (Uroxatral®)
- dihydroergotamine (D.H.E. 45®, Embolex®, Migranal®), ergonovine, ergotamine (Cafergot®,Ergomar®) methylergonovine
- cisapride
- pimozide (Orap®)
- oral midazolam, triazolam (Halcion®)
- the herbal supplement St. John's Wort (Hypericum perforatum)
- the cholesterol lowering medicines lovastatin (Mevacor®, Altoprev®, Advicor®) or simvastatin (Zocor®, Simcor®, Vytorin®)
- rifampin (Rifadin®, Rifater®, Rifamate®, Rimactane®)
- sildenafil (Revatio®) only when used for the treatment of pulmonary arterial hypertension.

Serious problems can happen if you or your child take any of these medicines with PREZISTA.

What should I tell my doctor before I take PREZISTA?

PREZISTA may not be right for you. Before taking PREZISTA, tell your healthcare provider if you:

- have liver problems, including hepatitis B or hepatitis C
- are allergic to sulfa medicines
- have high blood sugar (diabetes)
- have hemophilia
- are pregnant or planning to become pregnant. It is not known if PREZISTA will harm your unborn baby.
  Pregnancy Registry: You and your healthcare provider will need to decide if taking PREZISTA is right for you. If you take PREZISTA while you are pregnant, talk to your healthcare provider about how you can be included in the Antiretroviral Pregnancy Registry. The purpose of the registry is follow the health of you and your baby.
- are breastfeeding or plan to breastfeed. Do not breastfeed. We do not know if PREZISTA can be passed to your baby in your breast milk and whether it could harm your baby. Also, mothers with HIV-1 should not breastfeed because HIV-1 can be passed to the baby in the breast milk.

Tell your healthcare provider about all the medicines you take including prescription and nonprescription medicines, vitamins, and herbal supplements. Using PREZISTA and certain other medicines may affect each other causing serious side effects. PREZISTA may affect the way other medicines work and other medicines may affect how PREZISTA works.

Especially tell your healthcare provider if you take:

- medicine to treat HIV
- estrogen-based contraceptives (birth control). PREZISTA might reduce the effectiveness of estrogen-based contraceptives. You must take additional precautions for birth control such as a condom.
- medicine for your heart such as bepridil, lidocaine (Xylocaine Viscous®), quinidine (Nuedexta®) , amiodarone (Pacerone®, Cardarone®), digoxin (Lanoxin®), flecainide (Tambocor®), propafenone (Rythmol®)
- warfarin (Coumadin®, Jantoven®)
- medicine for seizures such as carbamazepine (Carbatrol®, Equetro®, Tegretol®, Epitol®), phenobarbital, phenytoin (Dilantin®, Phenytek®)
- medicine for depression such as trazadone and desipramine (Norpramin®)
- clarithromycin (Prevpac®, Biaxin®)
- medicine for fungal infections such as ketoconazole (Nizoral®), itraconazole (Sporanox®, Onmel®), voriconazole (VFend®)
- colchicine (Colcrys®, Col-Probenecid®)
- rifabutin (Mycobutin®)
- medicine used to treat blood pressure, a heart attack, heart failure, or to lower pressure in the eye such as metoprolol (Lopressor®, Toprol-XL®), timolol (Cosopt®, Betimol®, Timoptic®, Isatolol®, Combigan®)
- midazolam administered by injection
- medicine for heart disease such as felodipine (Plendil®), nifedipine
  (Procardia®, Adalat CC®, Afeditab CR®), nicardipine (Cardene®)
- steroids such as dexamethasone, fluticasone (Advair Diskus®, Veramyst®, Flovent®, Flonase®)
- bosentan(Tracleer®)
- medicine to treat chronic hepatitis C such as boceprevir (Victrelis™), telaprevir (Incivek™)
- medicine for cholesterol such as pravastatin (Pravachol®), atorvastatin (Lipitor®), rosuvastatin (Crestor®)
- medicine to prevent organ transplant failure such as cyclosporine
  (Gengraf®, Sandimmune®, Neoral®), tacrolimus (Prograf®), sirolimus (Rapamune®)
- salmeterol (Advair®, Serevent®)
- medicine for narcotic withdrawal such as methadone (Methadose®, Dolophine Hydrochloride), buprenorphine (Butrans®, Buprenex®, Subutex®), buprenorphine/naloxone (Suboxone®)
- medicine to treat schizophrenia such as risperidone (Risperdal®), thioridazine
- medicine to treat erectile dysfunction or pulmonary hypertension such as sildenafil (Viagra®, Revatio®), vardenafil (Levitra®, Staxyn®), tadalafil (Cialis®, Adcirca®)
- medicine to treat anxiety, depression or panic disorder such as sertraline (Zoloft®), paroxetine (Paxil®)

This is not a complete list of medicines that you should tell your healthcare provider that you are taking. Ask your healthcare provider or pharmacist if you are not sure if your medicine is one that is listed above. Know the medicines you take. Keep a list of them to show your doctor or pharmacist when you get a new medicine. Do not start any new medicines while you are taking PREZISTA without first talking with your healthcare provider.

How should I take PREZISTA?

- Take PREZISTA every day exactly as prescribed by your healthcare provider.
- You must take ritonavir (NORVIR®) at the same time as PREZISTA.
- Do not change your dose of PREZISTA or stop treatment without talking to your healthcare provider first.
- Take PREZISTA and ritonavir (NORVIR®) with food.
- Swallow PREZISTA tablets whole with a drink. If you have difficulty swallowing PREZISTA tablets, PREZISTA oral suspension is also available. Your health care provider will help determine whether PREZISTA tablets or oral suspension is right for you.
- PREZISTA oral suspension should be given with the supplied oral dosing syringe. Shake the suspension well before each usage.
- If your child is taking PREZISTA, your child's healthcare provider will decide the right dose based on your child's weight. Your child's healthcare provider will tell you how much PREZISTA (tablets or oral suspension) and how much ritonavir (NORVIR®) (capsules, tablets or solution) your child should take. Your child should take PREZISTA with ritonavir twice a day with food. If your child does not tolerate ritonavir oral solution, ask your child's healthcare provider for advice.
- If you take too much PREZISTA, call your healthcare provider or go to the nearest hosptial emergency room right away.

What should I do if I miss a dose?

People who take PREZISTA one time a day:

- If you miss a dose of PREZISTA by less than 12 hours, take your missed dose of PREZISTA right away. Then take your next dose of PREZISTA at your regularly scheduled time.
- If you miss a dose of PREZISTA by more than 12 hours, wait and then take the next dose of PREZISTA at your regularly scheduled time.

People who take PREZISTA two times a day

- If you miss a dose of PREZISTA by less than 6 hours, take your missed dose of PREZISTA right away. Then take your next dose of PREZISTA at your regularly scheduled time.
- If you miss a dose of PREZISTA by more than 6 hours, wait and then take the next dose of PREZISTA at your regularly scheduled time.

If a dose of PREZISTA is skipped, do not double the next dose. Do not take more or less than your prescribed dose of PREZISTA at any one time.

What are the possible side effects of PREZISTA?

PREZISTA can cause side effects including:

- See "What is the most important information I should know about PREZISTA?"
- Diabetes and high blood sugar (hyperglycemia). Some people who take protease inhibitors including PREZISTA can get high blood sugar, develop diabetes, or your diabetes can get worse. Tell your healthcare provider if you notice an increase in thirst or urinate often while taking PREZISTA.
- Changes in body fat. These changes can happen in people who take antiretroviral therapy. The changes may include an increased amount of fat in the upper back and neck ("buffalo hump"), breast, and around the back, chest, and stomach area. Loss of fat from the legs, arms, and face may also happen. The exact cause and long-term health effects of these conditions are not known.
- Changes in your immune system (Immune Reconstitution Syndrome) can happen when you start taking HIV medicines. Your immune system may get stronger and begin to fight infections that have been hidden in your body for a long time. Call your healthcare provider right away if you start having new symptoms after starting your HIV medicine.
- Increased bleeding for hemophiliacs. Some people with hemophilia have increased bleeding with protease inhibitors including PREZISTA.

The most common side effects of PREZISTA include:

- diarrhea
- nausea
- rash

- headache
- abdominal pain
- vomiting

Tell your healthcare provider if you have any side effect that bothers you or that does not go away.

These are not all of the possible side effects of PREZISTA. For more information, ask your health care provider.

Call your doctor for medical advice about side effects. You may report side effects to the FDA at 1-800-FDA-1088.

How should I store PREZISTA?

- Store PREZISTA oral suspension and tablets at room temperature [77°F (25°C)].
- Do not refrigerate or freeze PREZISTA oral suspension.
- Keep PREZISTA away from high heat.
- PREZISTA oral suspension should be stored in the original container.

Keep PREZISTA and all medicines out of the reach of children.

General information about PREZISTA

Medicines are sometimes prescribed for purposes other than those listed in a Patient Information leaflet. Do not use PREZISTA for a condition for which it was not prescribed. Do not give PREZISTA to other people even if they have the same condition you have. It may harm them.

This leaflet summarizes the most important information about PREZISTA. If you would like more information, talk to your healthcare provider. You can ask your healthcare provider or pharmacist for information about PREZISTA that is written for health professionals.

For more information, call 1-800-526-7736.

What are the ingredients in PREZISTA?

Active ingredient: darunavir

Inactive ingredients:

PREZISTA Oral Suspension: hydroxypropyl cellulose, microcrystalline cellulose, sodium carboxymethylcellulose, methylparaben sodium, citric acid monohydrate, sucralose, masking flavor, strawberry cream flavor,

hydrochloric acid (for pH adjustment), purified water.

PREZISTA 75 mg and 150 mg Tablets: colloidal silicon dioxide,

crospovidone, magnesium stearate, microcrystalline cellulose. The film

coating contains: OPADRY® White (polyethylene glycol 3350,

polyvinyl alcohol-partially hydrolyzed, talc, titanium dioxide).

PREZISTA 400 mg and 600 mg Tablets: colloidal silicon dioxide,

crospovidone, magnesium stearate, microcrystalline cellulose. The film

coating contains: OPADRY® Orange (FD&C Yellow No. 6, polyethylene glycol 3350, polyvinyl alcohol-partially hydrolyzed, talc, titanium dioxide).

This Patient Information has been approved by the U.S Food and Drug Administration.

Manufactured by:
PREZISTA Oral Suspension
Janssen Pharmaceutica, N.V.
Beerse, Belgium

PREZISTA Tablets
Janssen Ortho LLC, Gurabo, PR 00778

Manufactured for:
Janssen Therapeutics, Division of Janssen Products, LP, Titusville NJ 08560

NORVIR® is a registered trademark of its respective owner.

PREZISTA® is a registered trademark of Janssen Pharmaceuticals

© Janssen Pharmaceuticals, Inc. 2006

Revised: June 2012

INSTRUCTIONS FOR USE

PREZISTA® (pre-ZIS-ta)
(darunavir)
ORAL SUSPENSION

Be sure that you read, understand, and follow these Instructions for Use so that you measure and take PREZISTA Oral Suspension correctly. Ask your pharmacist or healthcare provider if you are not sure.

Each PREZISTA Oral Suspension carton contains:

- 1 bottle of PREZISTA Oral Suspension
- Oral dosing syringe
- 1 oral syringe adapter

Important information for use:

- Shake PREZISTA Oral Suspension well before each use.
- PREZISTA Oral Suspension should be given with the oral dosing syringe provided to make sure you measure the right amount. The oral dosing syringe provided with your PREZISTA Oral Suspension should not be used for any other medicines.

1. Shake the bottle.
  - Shake the bottle well before each use (See Figure A).

Figure A: Shake the bottle

2. Open the bottle of PREZISTA Oral Suspension.
  - Open the bottle by pushing downward on the cap and twisting it in the direction of the arrow (counter-clockwise) (See Figure B).

Figure B: Opening the bottle

3. The first time a bottle of PREZISTA Oral Suspension is used:
  - Insert the oral syringe adapter into the bottle. Press on the adapter until it is even with the top of the bottle (See Figure C).
  - Do not remove the oral syringe adapter from the bottle once inserted.

Figure C: Inserting the adapter

4. Insert the oral dosing syringe.
  - Fully push down (depress) the plunger of the syringe.
  - Insert the syringe into the opening in the oral syringe adapter until it is firmly in place (See Figure D).

Figure D: Inserting the syringe

5. Withdraw the prescribed amount of PREZISTA Oral Suspension.
  - Turn the bottle upside down. Gently pull back the plunger of the syringe until the bottom of the plunger is even with markings on the syringe for the prescribed dose (See Figure E). If air bubbles form in the syringe, empty the oral suspension in the syringe back into the bottle. Then repeat steps 4 and 5.

Figure E: Withdrawing the Oral Suspension

6. Turn the bottle right-side up and remove the syringe from the bottle by pulling straight up on the oral dosing syringe (See Figure F).

Figure F: Removing the syringe

7. Take the dose of PREZISTA.
  - Place the tip of the oral dosing syringe in the mouth.
  - Press on the plunger of the syringe towards the mouth (See Figure G).

Figure G: Taking the dose of PREZISTA

8. Close the bottle with the cap after use (See Figure H).

Figure H: Closing the bottle

9. Remove the plunger from the barrel, rinse both with water and allow to air dry after each use (See Figure I).

Figure I: Rinsing the syringe

10. Put the oral dosing syringe back together after air drying and store with PREZISTA Oral Suspension (See Figure J).

Figure J: Putting the syringe back together

How should I store PREZISTA?

- Store PREZISTA Oral Suspension and the oral dosing syringe at room temperature 77°F (25°C).
- Do not refrigerate or freeze PREZISTA Oral Suspension.
- Keep PREZISTA Oral Suspension away from high heat.
- Store PREZISTA Oral Suspension in the original container.

Keep PREZISTA and all medicines out of the reach of children.

This Instruction for Use has been approved by the U.S. Food and Drug Administration.

Manufactured by:
Janssen Pharmaceutica, N.V.
Beerse, Belgium

Manufactured for:
Janssen Therapeutics, Division of Janssen Products, LP, Titusville NJ 08560

© Janssen Pharmaceuticals, Inc. 2006

Issued December 2011

PRINCIPAL DISPLAY PANEL - 400 mg Tablet Bottle Label

60 Tablets

NDC 54868-5969-0

PREZISTA®
(darunavir) tablets

400 mg

Each tablet contains darunavir
ethanolate equivalent to 400 mg
of darunavir.

Rx only

PRINCIPAL DISPLAY PANEL - 600 mg Tablet Bottle Label

60 Tablets

NDC 54868-6369-0

PREZISTA®
(darunavir) tablets

600 mg

Each tablet contains darunavir
ethanolate equivalent to 600 mg
of darunavir.

Rx only